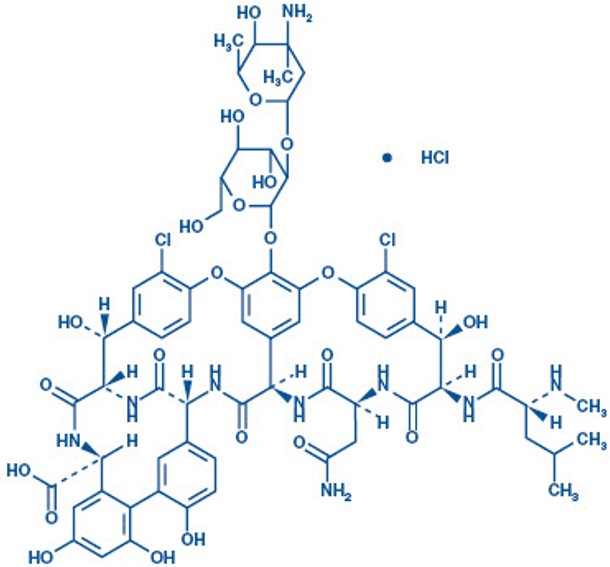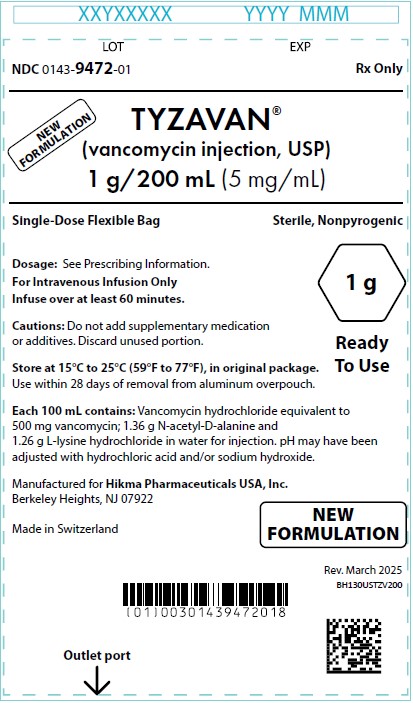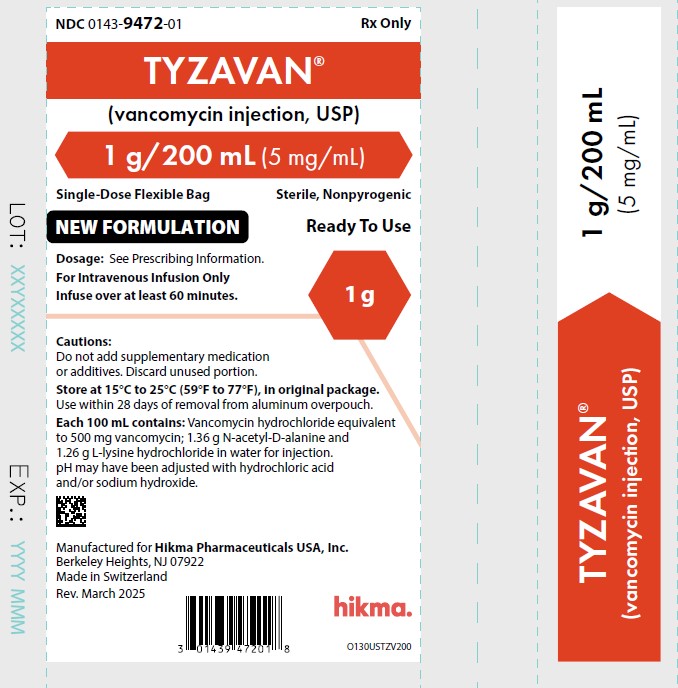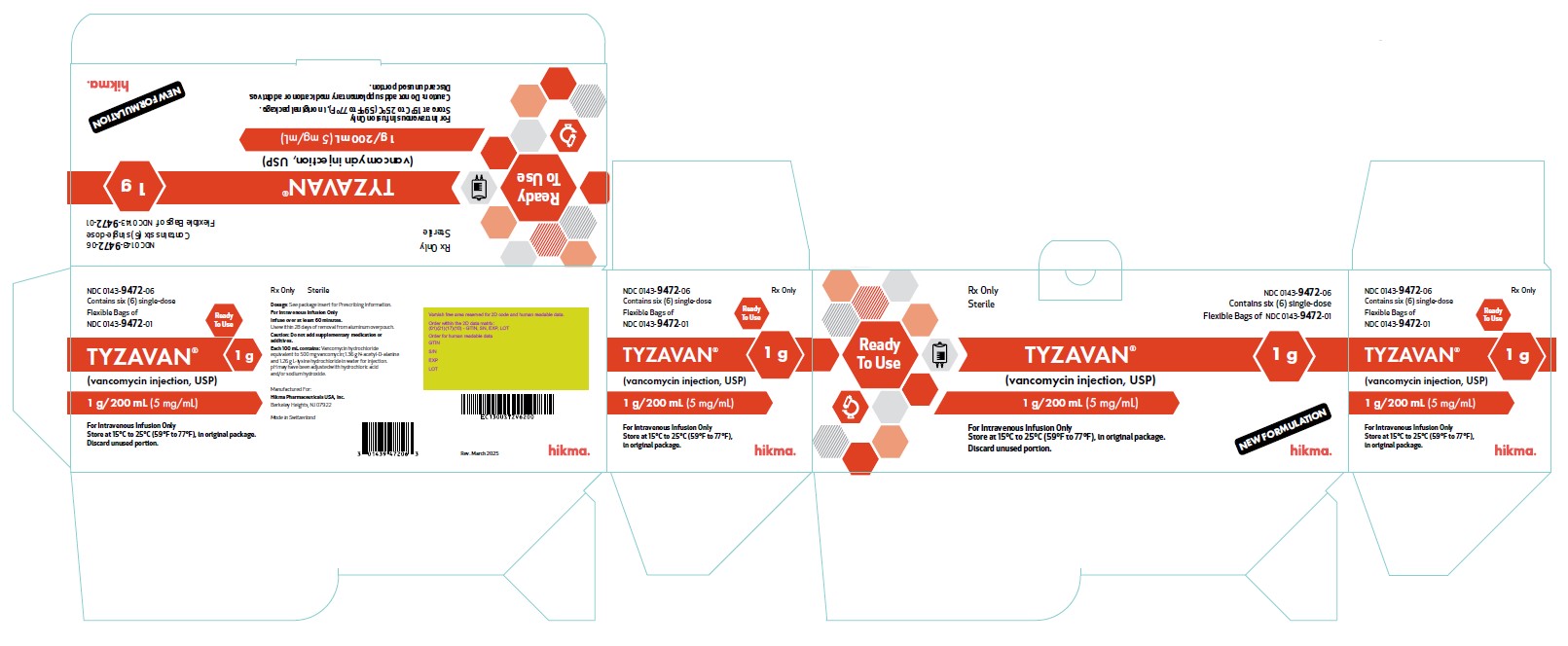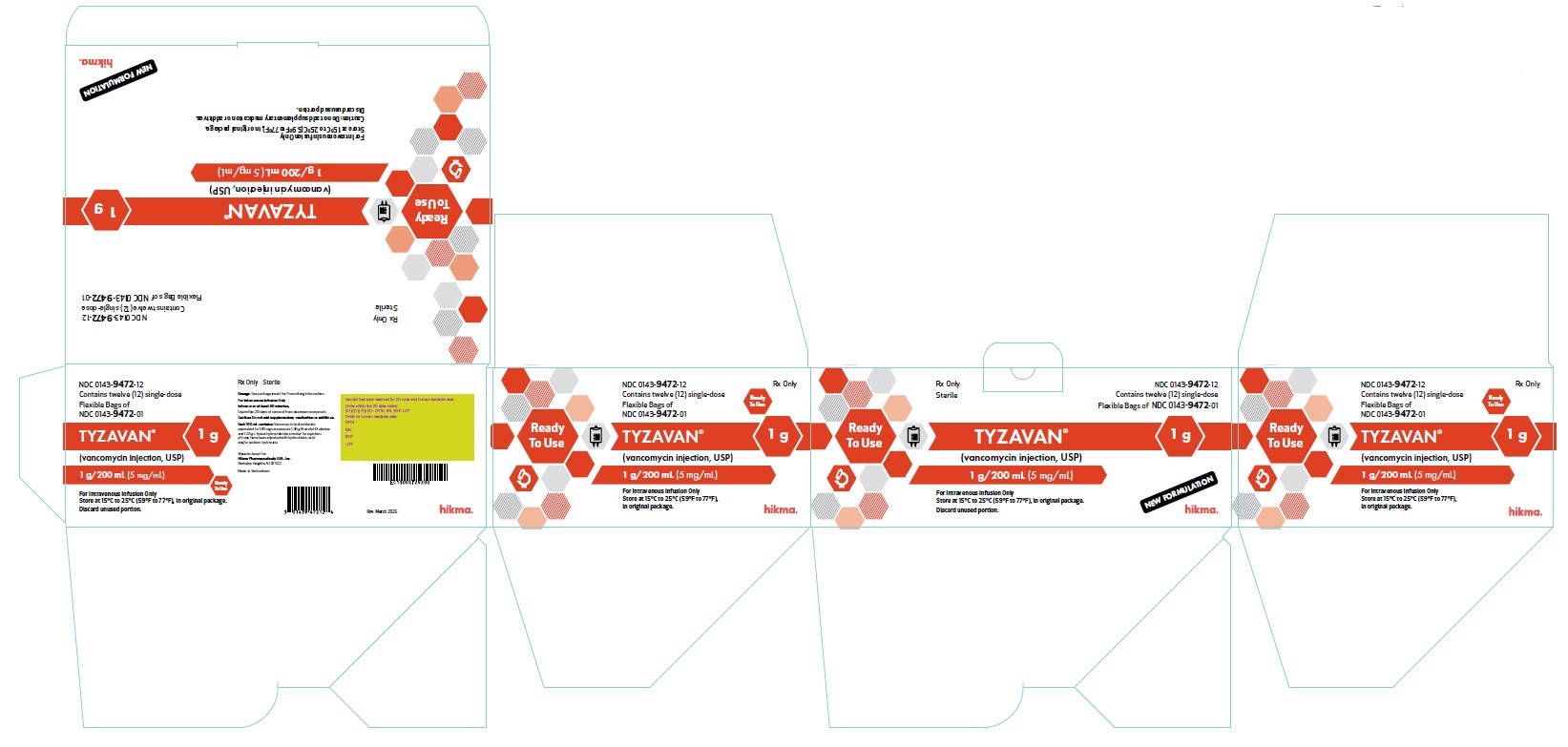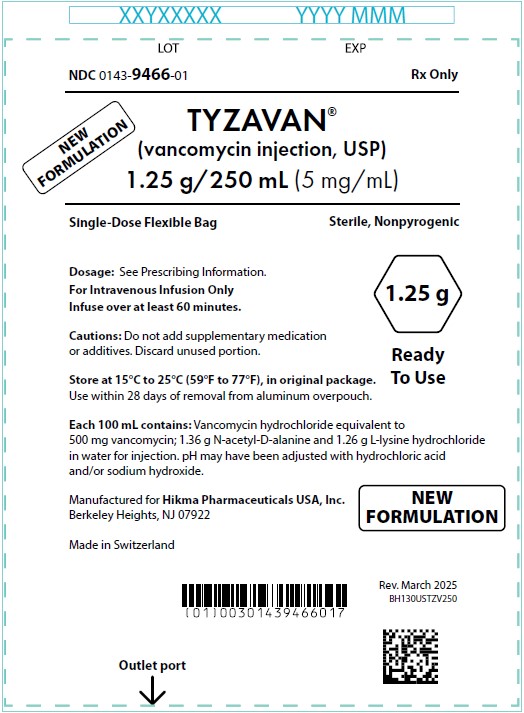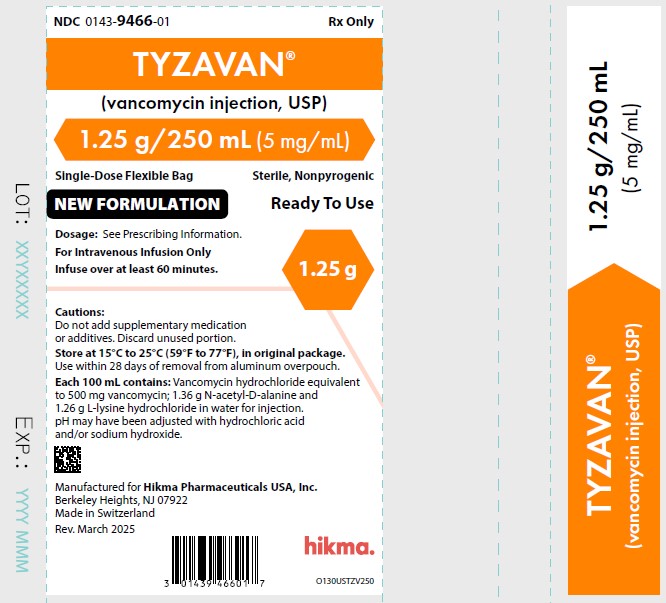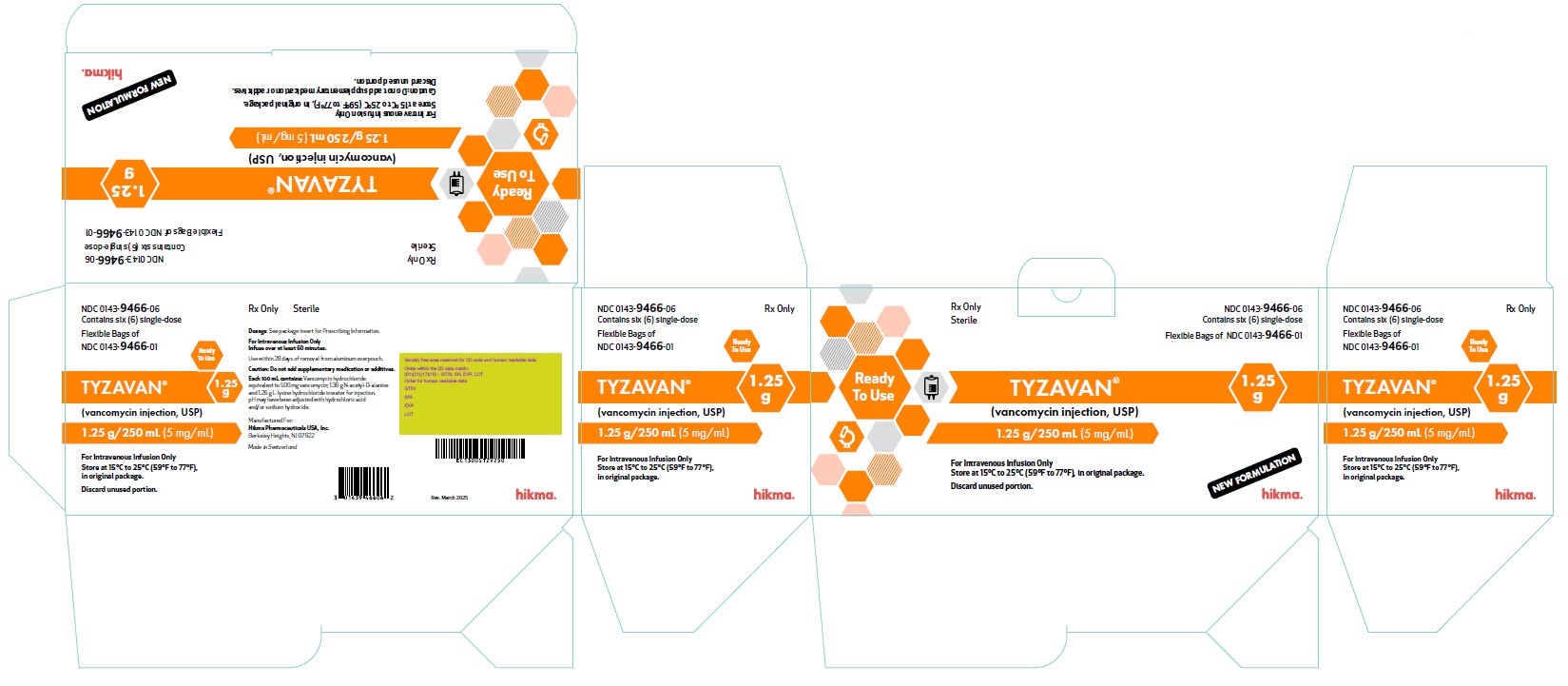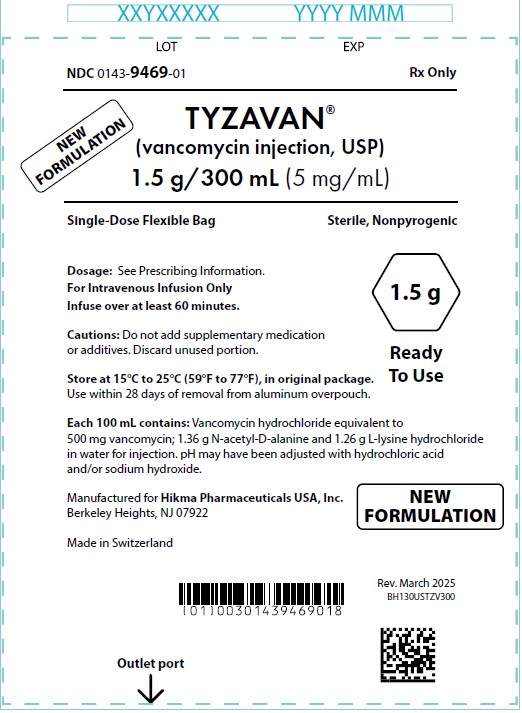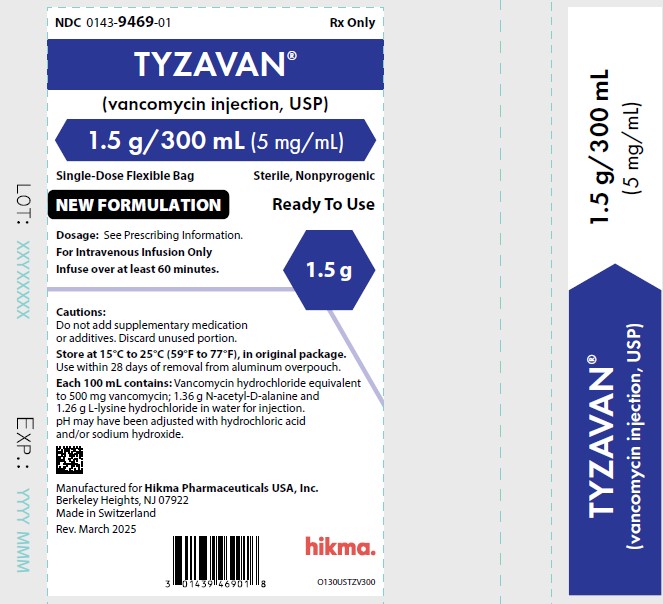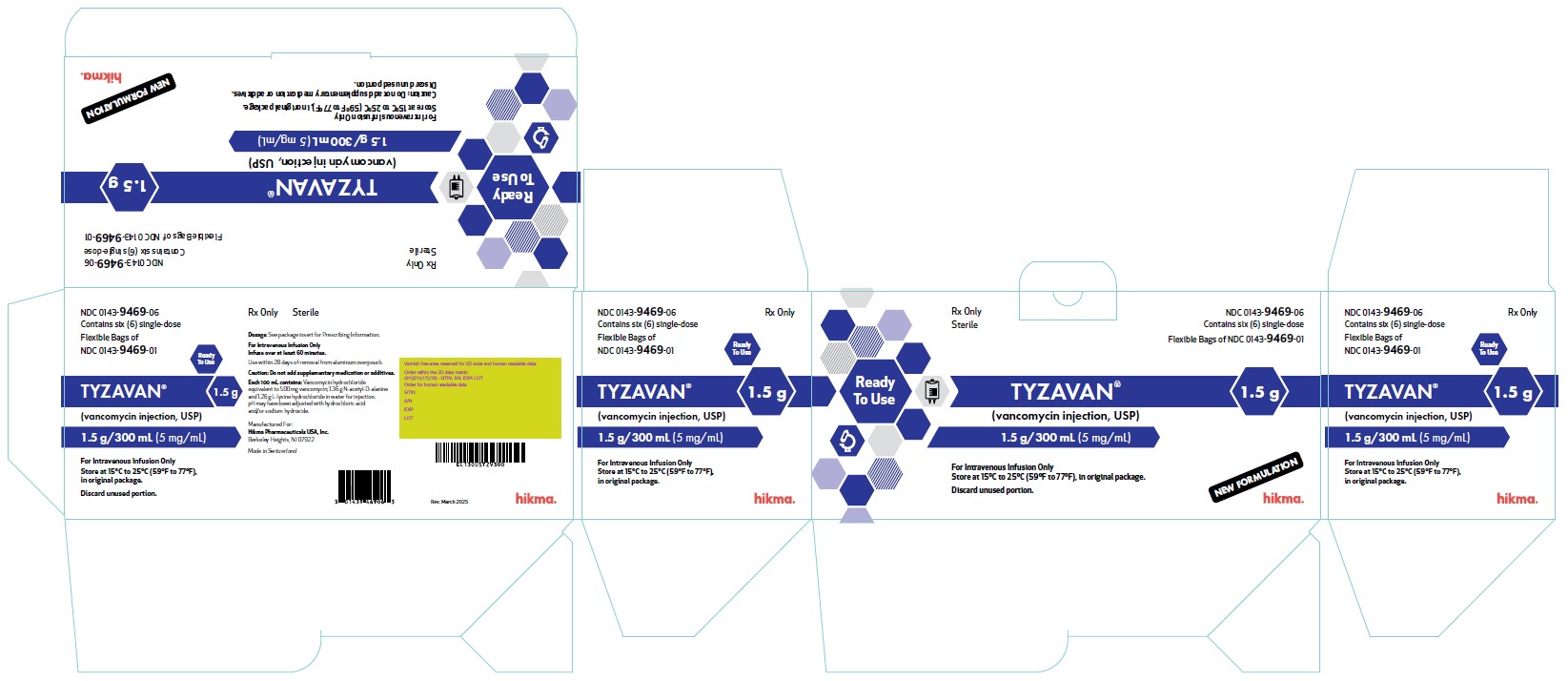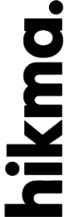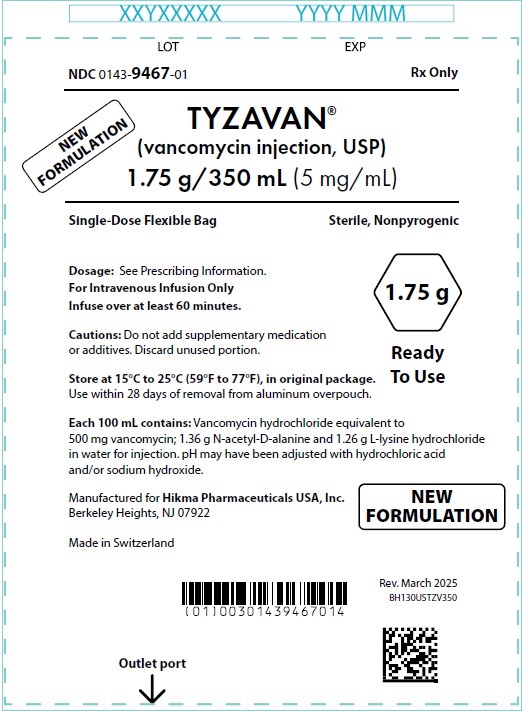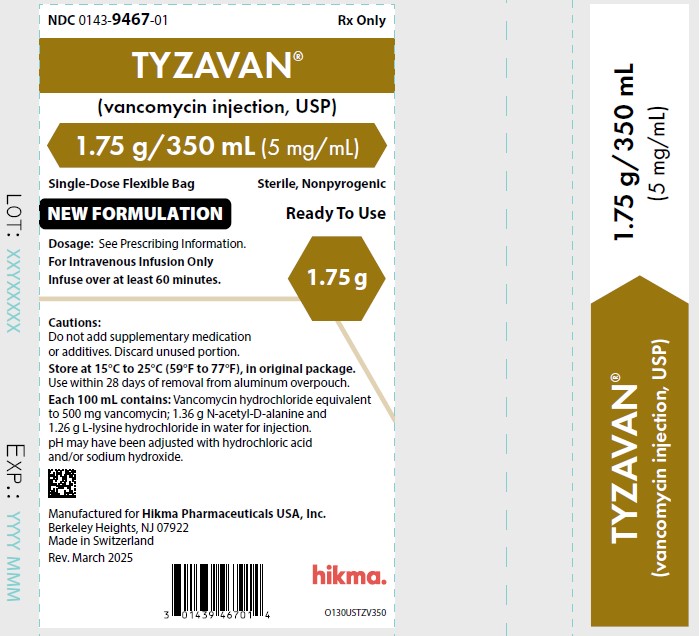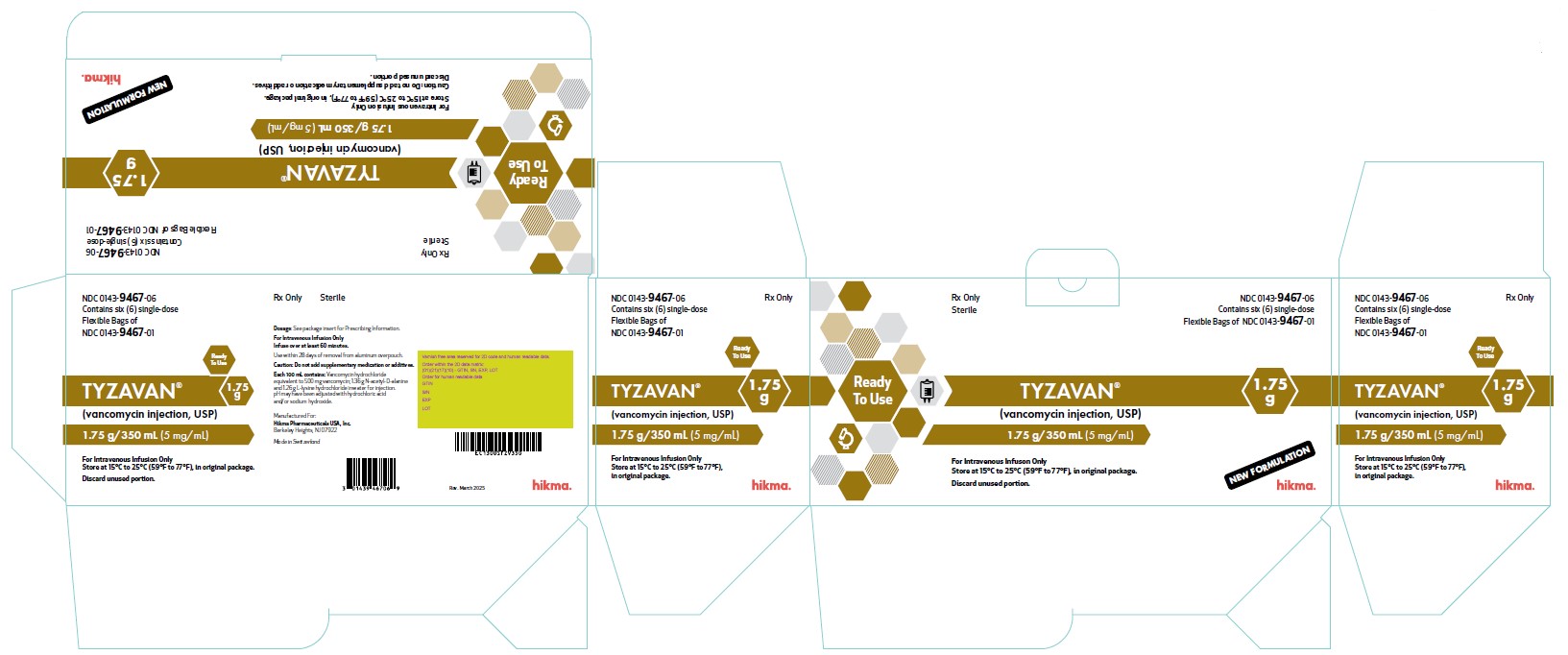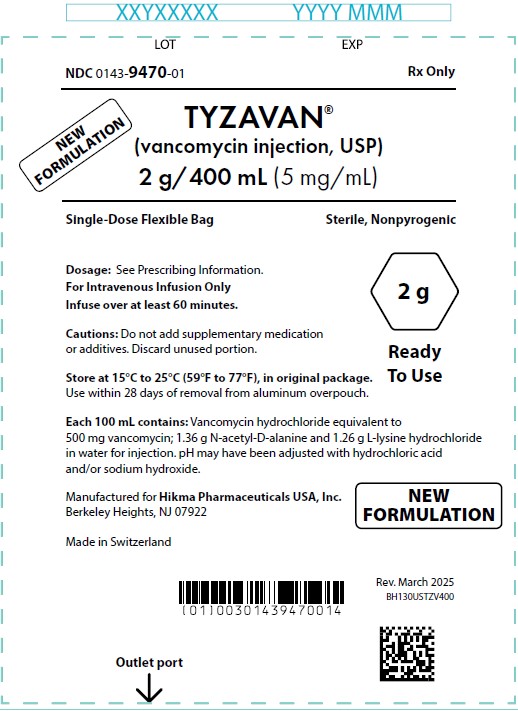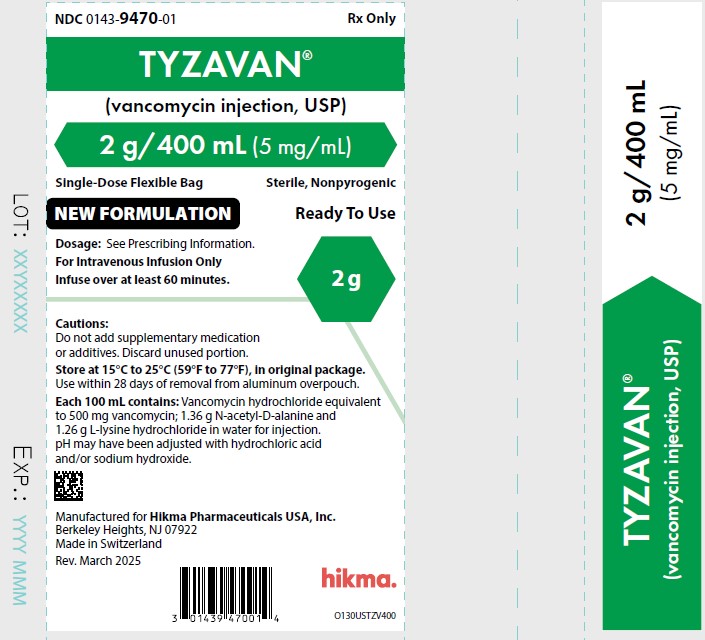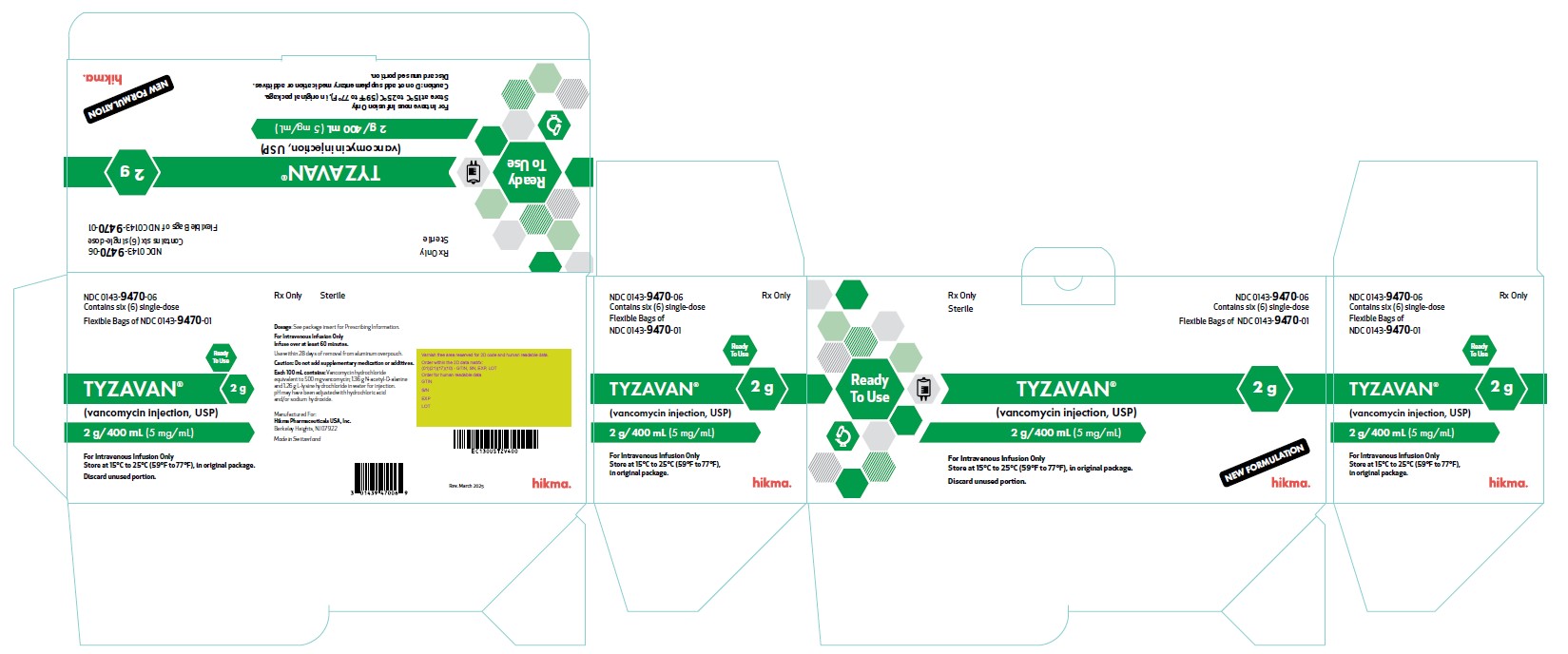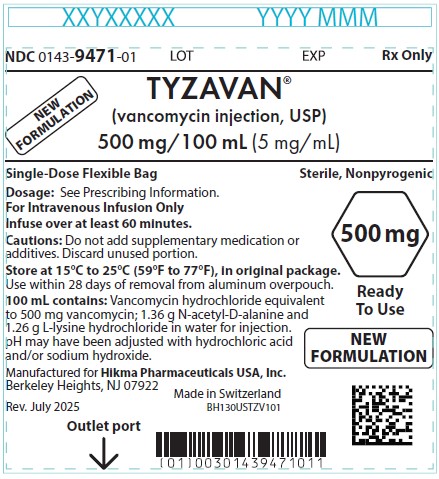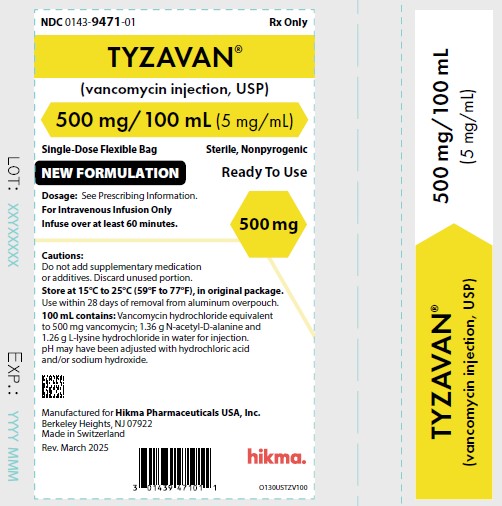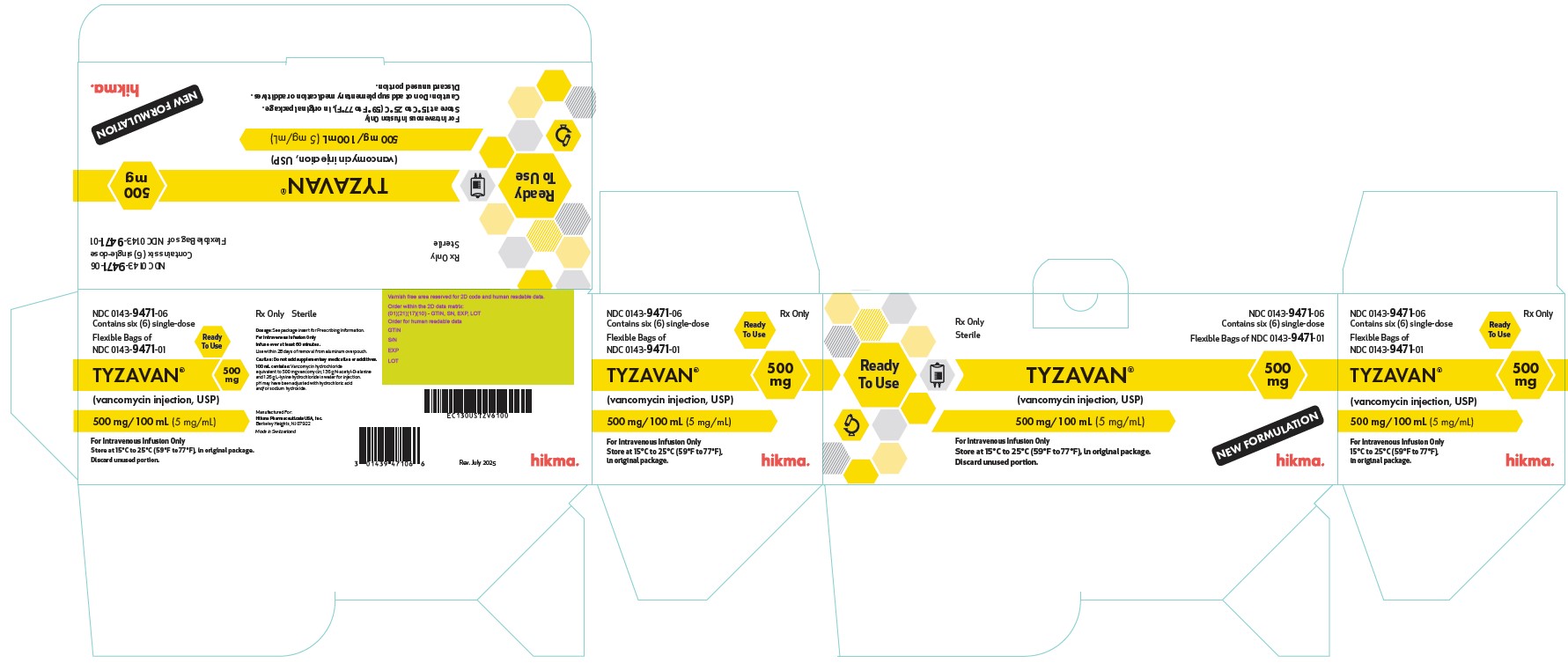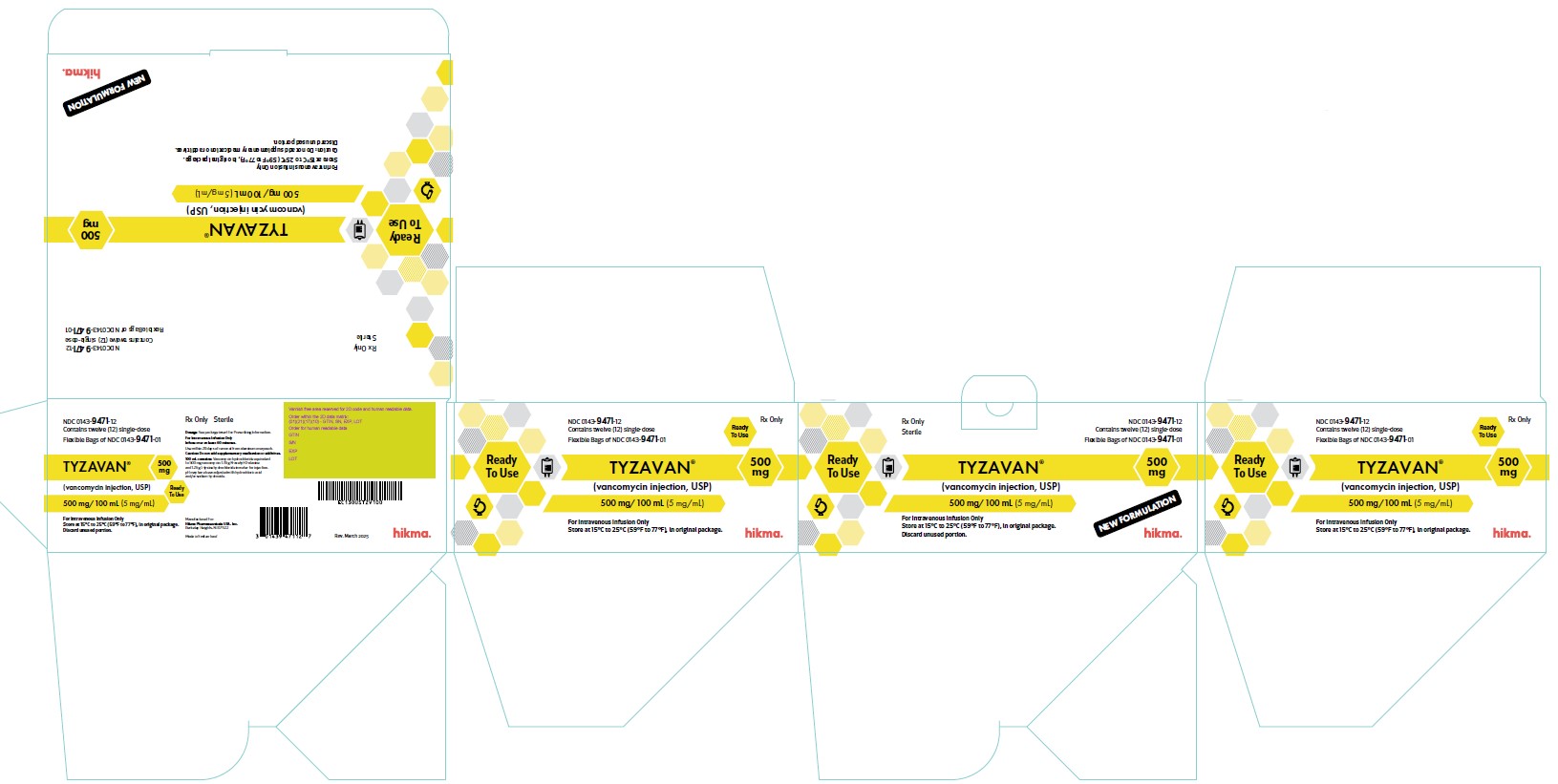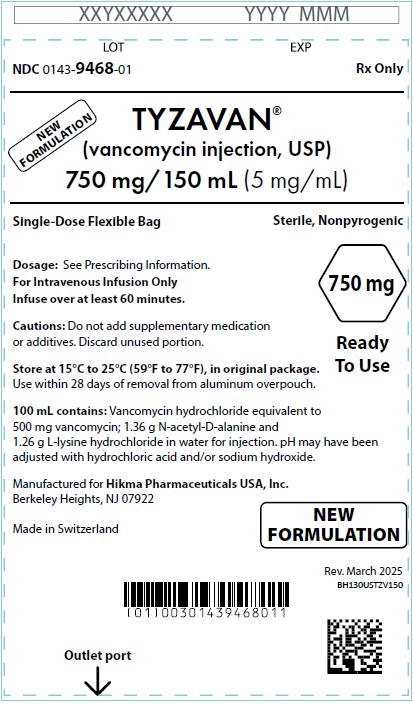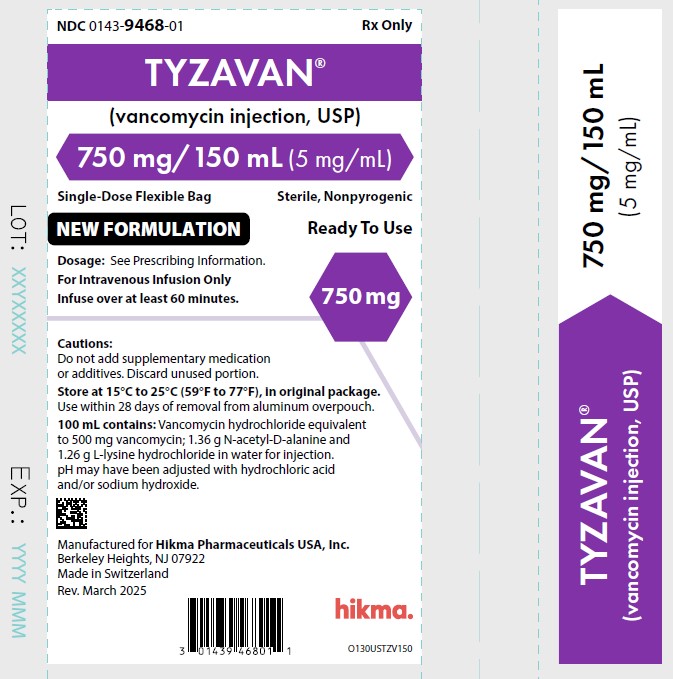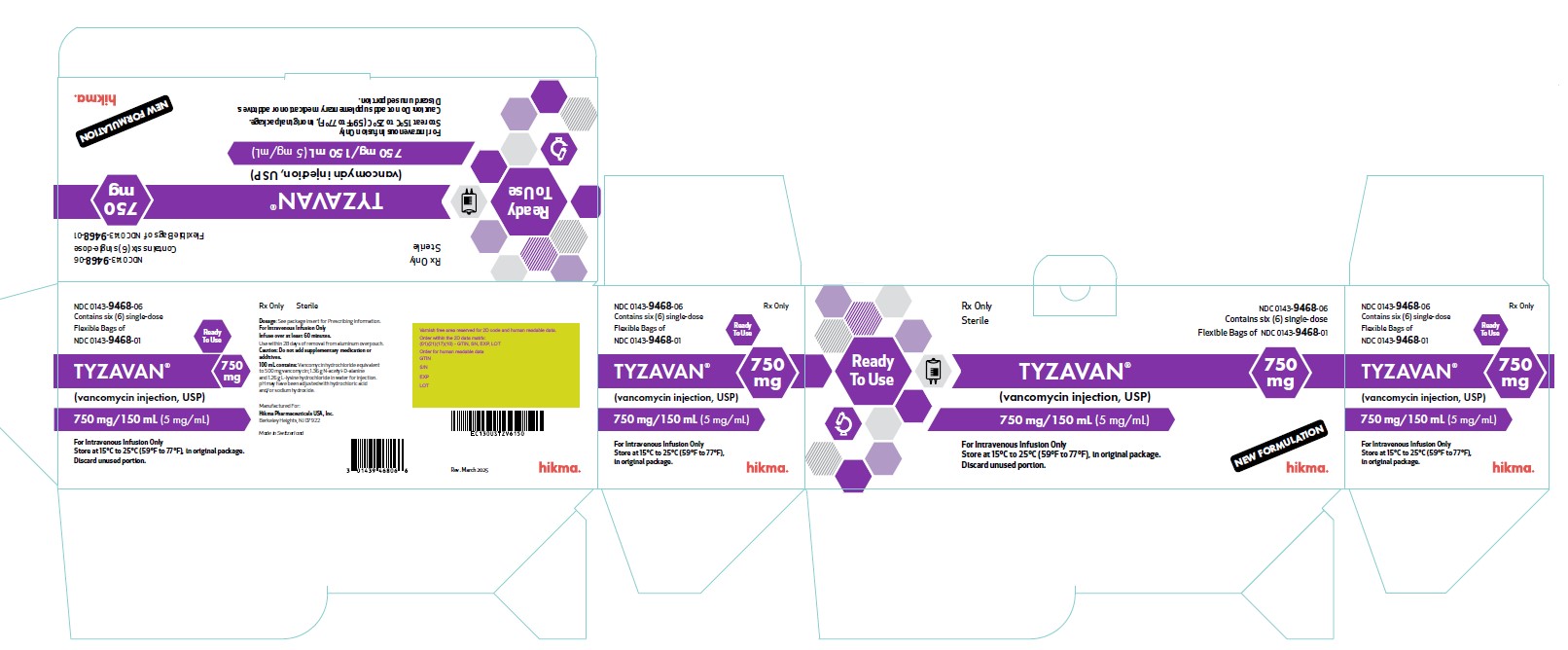 DRUG LABEL: TYZAVAN
NDC: 0143-9471 | Form: INJECTION, SOLUTION
Manufacturer: Hikma Pharmaceuticals USA Inc.
Category: prescription | Type: HUMAN PRESCRIPTION DRUG LABEL
Date: 20251028

ACTIVE INGREDIENTS: VANCOMYCIN 500 mg/100 mL
INACTIVE INGREDIENTS: N-ACETYL-D-ALANINE; LYSINE HYDROCHLORIDE; HYDROCHLORIC ACID; SODIUM HYDROXIDE

HIGHLIGHTS OF PRESCRIBING INFORMATION

These highlights do not include all the information needed to use TYZAVAN, safely and effectively. See full prescribing information for TYZAVAN.
TYZAVAN (vancomycin injection), for intravenous use
Initial U.S. Approval: 1958

RECENT MAJOR CHANGES

Boxed Warning | Removed 6/2025
Indications and Usage (1.1-1.5) | 6/2025
Dosage and Administration (2.1, 2.3) | 6/2025
Warnings and Precautions (5.1, 5.2) | 6/2025

1 INDICATIONS AND USAGE

TYZAVAN is a glycopeptide antibacterial indicated for the treatment of the following infections in adult and pediatric patients (1 month and older) for whom appropriate dosing with this formulation can be achieved:

- Septicemia (1.1)
- Infective Endocarditis (1.2)
- Skin and Skin Structure Infections (1.3)
- Bone Infections (1.4)
- Lower Respiratory Tract Infections (1.5)

To reduce the development of drug-resistant bacteria and maintain the effectiveness of TYZAVAN and other antibacterial drugs, TYZAVAN should be used only to treat or prevent infections that are proven or strongly suspected to be caused by bacteria. (1.6)

2 DOSAGE AND ADMINISTRATION

- If a dose of TYZAVAN is required that does not equal 500 mg, 750 mg, 1 g, 1.25 g, 1.5 g, 1.75 g or 2 g, this product is not recommended for use and an alternative formulation of vancomycin should be considered. (2.1).
- For intravenous use only. Do not administer orally (2.1).
- Administer TYZAVAN by intravenous infusion over 60 minutes or greater to reduce the risk of infusion reactions (2.1)
- Recommended Dosage in Adult Patients with Normal Renal Function: 2 g divided either as 0.5 grams (g) every 6 hours or 1 g every 12 hours (2.2)
- Recommended Dosage in Pediatric Patients (1 Month and Older) with Normal Renal Function: 10 mg/kg per dose given every 6 hours (2.3)
- Recommended Dosage in Patients with Renal Impairment: See full prescribing information for recommended doses in patients with renal impairment (2.4)
- See full prescribing information for further important preparation and administration instructions (2.1, 2.5)

3 DOSAGE FORMS AND STRENGTHS

Injection: TYZAVAN contains 500 mg vancomycin in 100 mL, 750 mg vancomycin in 150 mL, 1 g vancomycin in 200 mL, 1.25 g vancomycin in 250 mL, 1.5 g vancomycin in 300 mL, 1.75 g vancomycin in 350 mL and 2 g vancomycin in 400 mL (5 mg/mL) of Water for Injection in single-dose flexible bags. (3)

4 CONTRAINDICATIONS

Hypersensitivity to vancomycin (4)

5 WARNINGS AND PRECAUTIONS

- Infusion Reactions: Hypotension, including shock and cardiac arrest, wheezing, dyspnea, urticaria, muscular and chest pain and “vancomycin infusion reactions” which manifests as pruritus and erythema that involves the face, neck and upper body may occur with rapid intravenous administration. To reduce the risk of infusion reactions, administer TYZAVAN over a period of 60 minutes or greater and also prior to intravenous anesthetic agents. (2.1, 5.1)
- Nephrotoxicity: Monitor renal function in all patients receiving TYZAVAN. (5.2)
- Ototoxicity: Serial tests of auditory function may be helpful. (5.3)
- Severe Dermatologic Reactions: Discontinue TYZAVAN at the first appearance of signs and symptoms of TEN, SJS, DRESS, AGEP, or LABD. (5.4)
- Clostridioides difficile-Associated Diarrhea (CDAD): Evaluate patients if diarrhea occurs. (5.5).
- Neutropenia: Periodically monitor leukocyte count. (5.7)
- Phlebitis and Other Administration Site Reactions: Vancomycin is irritating to tissue and must be given by a secure intravenous route of administration. (5.8)

6 ADVERSE REACTIONS

The most common adverse reactions are anaphylaxis, “vancomycin infusion reactions”, acute kidney injury, hearing loss, neutropenia. (6)

To report SUSPECTED ADVERSE REACTIONS, contact Hikma Pharmaceuticals USA Inc. at 1-877-845-0689 or FDA at 1-800-FDA-1088 or www.fda.gov/medwatch.

7 DRUG INTERACTIONS

- Anesthetic Agents: Concomitant administration of vancomycin and anesthetic agents has been associated with erythema and histamine-like flushing. (2.1, 7.1)
- Piperacillin/Tazobactam: Increased incidence of acute kidney injury in patients receiving concomitant piperacillin/tazobactam and vancomycin as compared to vancomycin alone. Monitor kidney function in patients. (7.2)

FULL PRESCRIBING INFORMATION

1 INDICATIONS AND USAGE

1.1 Septicemia

TYZAVAN is indicated in adults and pediatric patients (1 month and older) for whom appropriate dosing with this formulation can be achieved [see Dosage and Administration (2) and Use in Specific Populations (8.4)] for the treatment of septicemia due to:

- Susceptible isolates of methicillin-resistant Staphylococcus aureus (MRSA) and coagulase negative staphylococci.
- Methicillin-susceptible staphylococci in penicillin-allergic patients, or those patients who cannot receive or who have failed to respond to other drugs, including penicillins or cephalosporins.

1.2 Infective Endocarditis

TYZAVAN is indicated in adults and pediatric patients (1 month and older) for whom appropriate dosing with this formulation can be achieved [see Dosage and Administration (2) and Use in Specific Populations (8.4)] for the treatment of infective endocarditis due to:

- Susceptible isolates of MRSA.
- Viridans group streptococci Streptococcus gallolyticus (previously known as Streptococcus bovis), Enterococcus species and Corynebacterium species. For enterococcal endocarditis, use TYZAVAN in combination with an aminoglycoside.
- Methicillin-susceptible staphylococci in penicillin-allergic patients, or those patients who cannot receive or who have failed to respond to other drugs, including penicillins or cephalosporins.

TYZAVAN is indicated in adults and pediatric patients (1 month and older) for whom appropriate dosing with this formulation can be achieved [see Dosage and Administration (2) and Use in Specific Populations (8.4)] for the treatment of early-onset prosthetic valve endocarditis caused by Staphylococcus epidermidis in combination with rifampin and an aminoglycoside.

1.3 Skin and Skin Structure Infections

TYZAVAN is indicated in adults and pediatric patients (1 month and older) for whom appropriate dosing with this formulation can be achieved [see Dosage and Administration (2) and Use in Specific Populations (8.4)] for the treatment of skin and skin structure infections due to:

- Susceptible isolates of MRSA and coagulase negative staphylococci.
- Methicillin-susceptible staphylococci in penicillin-allergic patients, or those patients who cannot receive or who have failed to respond to other drugs, including penicillins or cephalosporins.

1.4 Bone Infections

TYZAVAN is indicated in adults and pediatric patients (1 month and older) for whom appropriate dosing with this formulation can be achieved [see Dosage and Administration (2) and Use in Specific Populations (8.4)] for the treatment of bone infections due to:

- Susceptible isolates of MRSA and coagulase negative staphylococci.
- Methicillin-susceptible staphylococci in penicillin-allergic patients, or those patients who cannot receive or who have failed to respond to other drugs, including penicillins or cephalosporins.

1.5 Lower Respiratory Tract Infections

TYZAVAN is indicated in adults and pediatric patients (1 month and older) for whom appropriate dosing with this formulation can be achieved [see Dosage and Administration (2) and Use in Specific Populations (8.4)] for the treatment of lower respiratory tract infections due to:

- Susceptible isolates of MRSA
- Methicillin-susceptible staphylococci in penicillin-allergic patients, or those patients who cannot receive or who have failed to respond to other drugs, including penicillins or cephalosporins.

1.6 Usage

To reduce the development of drug-resistant bacteria and maintain the effectiveness TYZAVAN and other antibacterial drugs, TYZAVAN should be used only to treat or prevent infections that are proven or strongly suspected to be caused by susceptible bacteria. When culture and susceptibility information are available, they should be considered in selecting or modifying antibacterial therapy. In the absence of such data, local epidemiology and susceptibility patterns may contribute to the empiric selection of therapy.

2 DOSAGE AND ADMINISTRATION

2.1 Important Administration Instructions

- If a dose of TYZAVAN is required that does not equal 500 mg, 750 mg, 1 g, 1.25 g, 1.5 g, 1.75 g or 2 g, this product is not recommended for use and an alternative formulation of vancomycin should be considered.
  - TYZAVAN is intended for intravenous use only.
  - TYZAVAN is not to be administered orally.
  - To reduce the risk of infusion related adverse reactions, administer TYZAVAN by intravenous infusion over 60 minutes or greater [see Warnings and Precautions (5.1) and Adverse Reactions (6.1)]. An infusion rate of 10 mg/min or less is associated with fewer infusion-related adverse reactions [see Warnings and Precautions (5.1)]. Infusion related adverse reactions may occur, however, at any rate or concentration.
  - Drug additives should not be made to this solution.
  - TYZAVAN concentrations of no more than 5 mg/mL are recommended in adults and pediatric patients (1 month and older) [see Dosage and Administration (2.2)]. See also age-specific recommendations [see Dosage and Administration (2.3)].
  - Administer TYZAVAN by a secure intravenous route of administration to reduce the risk of local irritation and phlebitis reactions [see Warnings and Precautions (5.8)].
  - Administer TYZAVAN prior to intravenous anesthetic agents to reduce the risk of infusion related adverse reactions [see Warnings and Precautions (5.1)].

2.2 Recommended Dosage in Adult Patients with Normal Renal Function

The usual daily intravenous dosage of TYZAVAN is 2 grams (g) divided either as 500 mg every 6 hours or 1 g every 12 hours. Administer each dose by intravenous infusion over a period of 60 minutes or greater. Other patient factors, such as age or obesity, may call for modification of the usual intravenous daily dose. The initial daily dose should be no less than 15 mg/kg.

2.3 Recommended Dosage in Pediatric Patients (1 Month and Older) with Normal Renal Function

If a dose of TYZAVAN is required that does not equal 500 mg, 750 mg, 1 g, 1.25 g, 1.5 g, 1.75 g or 2 g, this product is not recommended for use and an alternative formulation of vancomycin should be considered [see Use in Specific Populations (8.4)].

Pediatric Patients (Aged 1 Month and Older)

The usual intravenous dosage of TYZAVAN is 10 mg/kg per dose given every 6 hours. Each dose should be administered over a period of at least 60 minutes. Close monitoring of serum concentrations of vancomycin may be warranted in these patients.

2.4 Recommended Dosage in Adult Patients with Renal Impairment

Dosage adjustment must be made in adult patients with renal impairment. The initial dose of TYZAVAN should be no less than 15 mg/kg in patients with any degree of renal impairment.

In the elderly, greater dosage reductions than expected may be necessary because of decreased renal function. Measure trough vancomycin serum concentrations to guide therapy, especially in seriously ill patients with changing renal function.

For functionally anephric patients, an initial dose of 15 mg/kg of body weight should be given to achieve prompt therapeutic serum concentration. A dose of 1.9 mg/kg/24 h should be given after the initial dose of 15 mg/kg. Measure vancomycin serum concentrations at 24 hours following the first dose to guide further intravenous therapy.

2.5 Administration and Preparation and Storage Instructions for TYZAVAN

Administration Instructions

TYZAVAN in transparent single-dose flexible bag is for intravenous administration only. Intermittent infusion is the recommended method of administration.

TYZAVAN is a room temperature stable, ready-to-use drug product.

Parenteral drug products should be inspected visually for particulate matter and discoloration prior to administration, whenever solution and container permit.

Preparation for Intravenous Administration and Storage Instructions:

1. Remove the flexible bag from aluminum overpouch.

2. Check for minute leaks by squeezing the bag firmly. If leaks are detected, discard solution because sterility may be impaired. Leaks may be more readily detected by wrapping the bag with blotting paper or a tissue before squeezing.

3. Do not add supplemental medication.

4. Visually inspect the flexible bag. If the outlet port protector is damaged, detached, or not present, discard the flexible bag as solution path sterility may be impaired. If after visual inspection the solution is cloudy or if an insoluble precipitate is noted or if any seals are not intact, the flexible bag should be discarded.

5. The solution in the flexible bag remains chemically stable for 28 days at room temperature (15°C - 25°C (59°F – 77ºF)) after removal from the aluminum overpouch. Discard unused drug.
6. Suspend the flexible bag from eyelet support.

7. Remove protector from outlet port at bottom of flexible bag.

8. Attach administration set. Refer to complete directions accompanying set.

9. Use sterile equipment.

Do not use flexible bags in series connections. Such use could result in an embolism due to residual air being drawn from the primary container before administration of the fluid from the secondary container is complete.

2.6 Incompatibilities for Intravenous Use

Vancomycin solution has a low pH and may cause chemical or physical instability when it is mixed with other compounds.

Mixtures of solutions of vancomycin and beta-lactam antibacterial drugs have been shown to be physically incompatible. The likelihood of precipitation increases with higher concentrations of vancomycin. It is recommended to adequately flush the intravenous lines between the administration of these antibacterial drugs.

3 DOSAGE FORMS AND STRENGTHS

Injection: TYZAVAN (Vancomycin Injection, USP) is a ready to use clear, colorless to light brown sterile solution in single-dose flexible bags in the following strengths: 500 mg vancomycin in 100 mL (5 mg/mL), 750 mg vancomycin in 150 mL (5 mg/mL), 1 g vancomycin in 200 mL (5 mg/mL), 1.25 g vancomycin in 250 mL (5 mg/mL), 1.5 g vancomycin in 300 mL (5 mg/mL), 1.75 g vancomycin in 350 mL (5 mg/mL) and 2 g vancomycin in 400 mL (5mg/mL) of Water for Injection [see Description (11)].

4 CONTRAINDICATIONS

TYZAVAN is contraindicated in patients with known hypersensitivity to vancomycin.

5 WARNINGS AND PRECAUTIONS

5.1 Infusion Reactions

Hypotension, including shock and cardiac arrest, wheezing, dyspnea, urticaria or pruritus, muscular and chest pain may occur with rapid TYZAVAN administration (e.g., over several minutes). The reactions may be more severe in pediatric patients (1 month and older) [see Use in Specific Populations (8.4)].

Rapid intravenous administration of TYZAVAN may also be associated with “vancomycin infusion reactions” which manifests as pruritus and erythema that involves the face, neck and upper body or pain and muscle spasm of the chest and back. There have been reports that the frequency of of infusion-related reactions (including hypotension, flushing, erythema, urticaria, and pruritus) increases with the concomitant administration of anesthetic agents.

Infusion-related adverse reactions are related to both the concentration and the rate of administration of TYZAVAN. Infusion-related adverse reactions may occur, however, at any rate or concentration.

Administer TYZAVAN over a period of 60 minutes or greater to reduce the risk of infusion-related adverse reactions. In selected patients in need of fluid restriction, a concentration up to 10 mg/mL may be used; use of such higher concentrations may increase the risk of infusion-related adverse reactions.

Administer TYZAVAN as a 60-minute infusion prior to administration of intravenous anesthetic agents when feasible to minimize infusion-related adverse reactions. Stop the infusion if a reaction occurs because this usually results in prompt cessation of these reactions.

5.2 Nephrotoxicity

TYZAVAN can result in acute kidney injury (AKI), including acute renal failure, mainly due to interstitial nephritis or less commonly acute tubular necrosis. AKI is manifested by increasing blood urea nitrogen (BUN) and serum creatinine (Cr). The risk of AKI increases with higher vancomycin serum levels, prolonged exposure, concomitant administration of other nephrotoxic drugs, concomitant administration of piperacillin-tazobactam [see Drug Interactions (7.2)], volume depletion, pre-existing renal impairment and in critically ill patients and patients with co-morbid conditions that predispose to renal impairment.

Monitor serum vancomycin concentrations and renal function in all patients receiving TYZAVAN. More frequent monitoring is recommended in patients with comorbidities that predispose to impairment in renal function or are concomitantly receiving other nephrotoxic drugs, in critically ill patients, in patients with changing renal function, and in patients requiring higher therapeutic vancomycin levels. If acute kidney injury occurs, discontinue TYZAVAN or reduce the dose [see Dosage and Administration (2.4)].

5.3 Ototoxicity

Ototoxicity has occurred in patients receiving vancomycin. It may be reversible or permanent. Ototoxicity manifests as tinnitus, hearing loss, dizziness or vertigo. The risk is higher in older patients, patients who are receiving higher doses, who have an underlying hearing loss, who are receiving concomitant therapy with another ototoxic agent, such as an aminoglycoside or who have underlying renal impairment. Monitor for signs and symptoms of ototoxicity during therapy. Monitor serum vancomycin concentrations and renal function in all patients receiving parenteral vancomycin. Discontinue TYZAVAN if ototoxicity occurs. Dosage of TYZAVAN must be adjusted for patients with renal impairment [see Dosage and Administration (2.3)]. Serial tests of auditory function may be helpful in order to minimize the risk of ototoxicity.

5.4 Severe Dermatologic Reactions

Severe dermatologic reactions such as toxic epidermal necrolysis (TEN), Stevens-Johnson syndrome (SJS), drug reaction with eosinophilia and systemic symptoms (DRESS), acute generalized exanthematous pustulosis (AGEP), and linear IgA bullous dermatosis (LABD) have been reported in association with the use of vancomycin. Cutaneous signs or symptoms reported include skin rashes (including exfoliative dermatitis), mucosal lesions, and blisters.

Discontinue TYZAVAN at the first appearance of signs and symptoms of TEN, SJS, DRESS, AGEP, or LABD.

5.5 Clostridioides Difficile-Associated Diarrhea (CDAD)

Clostridioides difficile-associated diarrhea (CDAD) has been reported with use of nearly all antibacterial agents, including vancomycin and may range in severity from mild diarrhea to fatal colitis. Treatment with antibacterial agents alters the normal flora of the colon leading to overgrowth of C. difficile.

C. difficile produces toxins A and B which contribute to the development of CDAD. Hypertoxin producing strains of C. difficile cause increased morbidity and mortality, as these infections can be refractory to antimicrobial therapy and may require colectomy. CDAD must be considered in all patients who present with diarrhea following antibacterial use. Careful medical history is necessary since CDAD has been reported to occur over two months after the administration of antibacterial agents.

If CDAD is suspected or confirmed, ongoing antibacterial use not directed against C. difficile may need to be discontinued. Appropriate fluid and electrolyte management, protein supplementation, antibacterial treatment of C. difficile, and surgical evaluation should be instituted as clinically indicated.

Prolonged use of TYZAVAN may result in the overgrowth of nonsusceptible microorganisms. Careful observation of the patient is essential. If superinfection occurs during therapy, appropriate measures should be taken. In rare instances, there have been reports of pseudomembranous colitis due to C. difficile developing in patients who received intravenous vancomycin.

5.6 Hemorrhagic Occlusive Retinal Vasculitis (HORV)

Hemorrhagic occlusive retinal vasculitis, including permanent loss of vision, occurred in patients receiving intracameral or intravitreal administration of vancomycin during or after cataract surgery. The safety and efficacy of vancomycin administered by the intracameral or the intravitreal route have not been established by adequate and well-controlled trials. Vancomycin is not indicated for the prophylaxis of endophthalmitis.

5.7 Neutropenia

Reversible neutropenia has been reported in patients receiving vancomycin [see Adverse Reactions (6.1)]. Patients who will undergo prolonged therapy with vancomycin or those who are receiving concomitant drugs that may cause neutropenia should have periodic monitoring of the leukocyte count.

Reversible neutropenia, usually starting 1 week or more after onset of therapy with vancomycin or after a total dosage of more than 25 g, has been reported for several dozen patients. Neutropenia appears to be promptly reversible when vancomycin is discontinued. Thrombocytopenia has been reported. Although a causal relationship has not been established, reversible agranulocytosis (granulocytes <500/mm^3) has been reported.

5.8 Phlebitis and Other Administration Site Reactions

Inflammation at the injection site has been reported. Vancomycin is irritating to tissue and must be given by a secure intravenous route of administration. Thrombophlebitis may occur, the frequency and severity of which can be minimized by slow infusion of the drug and by rotation of venous access sites.

Administration of TYZAVAN by intramuscular (IM), intraperitoneal, intrathecal (intralumbar or intraventricular), or intravitreal routes has not been approved and is not recommended. The safety and efficacy of vancomycin administered by these routes of administration have not been established by adequate and well controlled trials. Pain, tenderness, and necrosis occur with intramuscular (IM) injection of vancomycin or with inadvertent extravasation. There have been reports that the frequency of infusion-related events (including hypotension, flushing, erythema, urticaria, and pruritus) increases with the concomitant administration of anesthetic agents. Infusion-related events may be minimized by the administration of vancomycin of at least a 60-minute infusion prior to anesthetic induction.

Administration of sterile vancomycin by the intraperitoneal route during continuous ambulatory peritoneal dialysis (CAPD) has been reported to result in chemical peritonitis. Manifestations of this syndrome range from a cloudy dialysate alone to a cloudy dialysate accompanied by variable degrees of abdominal pain and fever. This syndrome appears to be resolved after discontinuation of intraperitoneal vancomycin.

About 60% of an intraperitoneal dose of vancomycin administered during peritoneal dialysis is absorbed systemically in 6 hours. Serum concentrations of about 10 mcg/mL are achieved by intraperitoneal injection of 30 mg/kg of vancomycin. However, the safety and efficacy of the intraperitoneal use of vancomycin has not been established in adequate and well-controlled trials.

5.9 Development of Drug-Resistant Bacteria

Prescribing TYZAVAN in the absence of a proven or strongly suspected bacterial infection or a prophylactic indication is unlikely to provide benefit to the patient and increases the risk of the development of drug-resistant bacteria.

6 ADVERSE REACTIONS

The following clinically significant adverse reactions are described elsewhere in the labeling:

- Infusion Reactions [see Warnings and Precautions (5.1)]
- Nephrotoxicity [see Warnings and Precautions (5.2)]
- Ototoxicity [see Warnings and Precautions (5.3)]
- Severe Dermatologic Reactions [see Warnings and Precautions (5.4)]
- Clostridioides Difficile-Associated Diarrhea [see Warnings and Precautions (5.5)]
- Hemorrhagic Occlusive Retinal Vasculitis [see Warnings and Precautions (5.6)]
- Neutropenia [see Warnings and Precautions (5.7)]
- Phlebitis and Other Administration Site Reactions [see Warnings and Precautions (5.8)]

6.1 Clinical Trials Experience

Because clinical trials are conducted under widely varying conditions, adverse reaction rates observed in the clinical trials of a drug cannot be directly compared to rates in the clinical trials of another drug and may not reflect the rates observed in practice. The following adverse reactions associated with the use of vancomycin were identified in clinical trials:

Immune System Disorders: Anaphylaxis and “vancomycin infusion reaction”

Renal and Urinary Disorders: Acute kidney injury and interstitial nephritis

Ear and Labyrinth Disorders: Hearing loss, vertigo, and tinnitus

Skin and Subcutaneous Tissue Disorders: Rashes including exfoliative dermatitis, and Stevens-Johnson syndrome (SJS)

Gastrointestinal Disorders: Clostridioides difficile colitis, nausea

Blood and Lymphatic System Disorders: Agranulocytosis, neutropenia, pancytopenia, leukopenia, thrombocytopenia, eosinophilia

Cardiac Disorders: Cardiac arrest, chest pain

General Disorders and Administration Site Conditions: General discomfort, fever, chills, phlebitis, injection site irritation, injection site pain and necrosis following intramuscular injection, chemical peritonitis following intraperitoneal administration (TYZAVAN is not approved for intramuscular and intraperitoneal administration)

Laboratory Abnormalities: Elevated blood urea nitrogen, elevated serum creatinine

Musculoskeletal and Connective Tissue Disorders: Muscle pain

Nervous System Disorders: Dizziness

Respiratory, Thoracic and Mediastinal Disorders: Wheezing, dyspnea

Vascular Disorders: Hypotension, shock, vasculitis

6.2 Postmarketing Experience

The following adverse reactions have been identified during postmarketing use of vancomycin. Because these reactions are reported voluntarily from a population of uncertain size, it is not possible to reliably estimate their frequency or establish a causal relationship to drug exposure.

Immune System Disorders: Acute myocardial ischemia with or without myocardial infarction may occur as part of an allergic reaction.

Skin and Subcutaneous Tissue Disorders: Severe dermatologic reactions such as toxic epidermal necrolysis (TEN), drug reaction with eosinophilia and systemic symptoms (DRESS), acute generalized exanthematous pustulosis (AGEP), and linear IgA bullous dermatosis (LABD).

7 DRUG INTERACTIONS

7.1 Anesthetic Agents

Concomitant administration of vancomycin and anesthetic agents has been associated with erythema and histamine-like flushing [see Warnings and Precautions (5.1) and Use in Specific Populations (8.4)].

7.2 Piperacillin-Tazobactam

Studies have detected an increased incidence of acute kidney injury in patients administered concomitant piperacillin/tazobactam and vancomycin as compared to vancomycin alone. Monitor kidney function in patients receiving concomitant piperacillin/tazobactam and TYZAVAN. No pharmacokinetic interactions have been noted between piperacillin/tazobactam and vancomycin.

7.3 Ototoxic and/or Nephrotoxic Drugs

Concurrent and/or sequential systemic or topical use of other potentially neurotoxic and/or nephrotoxic drugs with TYZAVAN requires more frequent monitoring of renal function.

8 USE IN SPECIFIC POPULATIONS

8.1 Pregnancy

Risk Summary

The available data on the use of this formulation of TYZAVAN (which includes the excipient NADA) in pregnant women are insufficient to evaluate for a drug-associated risk of major birth defects, miscarriage, or other adverse maternal or fetal outcomes (see Data). Available data over several decades of vancomycin (without the excipient NADA) use in pregnant women have not identified a drug-associated risk of major birth defects, miscarriage, or adverse maternal or fetal outcomes (see Data).

Vancomycin did not show adverse developmental effects when administered intravenously to pregnant rats and rabbits during organogenesis at doses less than or equal to the recommended maximum human dose (see Data).

The background risk of major birth defects and miscarriage for the indicated population is unknown. All pregnancies have a background risk of birth defect, loss, or other adverse outcomes. In the U.S. general population, the estimated background risk of major birth defects and miscarriage in clinically recognized pregnancies is 2 to 4% and 15 to 20%, respectively.

Data

Human Data

Available data from postmarketing cases on use of this formulation of vancomycin injection (with the excipient NADA) in pregnant women are insufficient to evaluate for a drug-associated risk of major birth defects, miscarriage, or other adverse maternal or infant outcomes.

There are no available data on first trimester use of vancomycin (without the excipient NADA); however, available published data on use in pregnancy during the second and third trimesters have not shown an association with adverse pregnancy related outcomes.

A published study evaluated hearing loss and nephrotoxicity in infants of 10 pregnant intravenous drug users treated with intravenously administered vancomycin (formulation did not include the excipient NADA) for suspected or documented methicillin-resistant Staphylococcus aureus (MRSA) in the second or third trimester. The comparison groups were 10 non-intravenous drug-dependent patients who received no treatment, and 10 untreated intravenous drug-dependent patients who served as substance abuse controls. No infant in the vancomycin exposed group had abnormal sensorineural hearing at 3 months of age or nephrotoxicity.

A published prospective study assessed outcomes in 55 pregnant women with a positive Group B streptococcus (GBS) culture and a high-risk penicillin allergy with resistance to clindamycin or unknown sensitivity who were administered vancomycin (formulation did not include the excipient NADA) at the time of delivery. Vancomycin dosing ranged from the standard 1 g intravenously every 12 hours to 20 mg/kg intravenous every 8 hours (maximum individual dose 2 g). No major adverse reactions were recorded either in the mothers or their newborns. None of the newborns had sensorineural hearing loss. Neonatal renal function was not examined, but all of the newborns were discharged in good condition.

Animal Data

Vancomycin did not cause fetal malformations when administered during organogenesis to pregnant rats (gestation days 6 to 15) and rabbits (gestation days 6 to 18) at doses less than or equal to the recommended maximum human dose (based on body surface area comparisons) of 200 mg/kg/day IV to rats or 120 mg/kg/day IV to rabbits. No effects on fetal weight or development were seen in rats at the highest dose tested or in rabbits given 80 mg/kg/day (approximately 1 and 0.8 times the recommended maximum human dose based on body surface area, respectively). Maternal toxicity was observed in rats (at doses 120 mg/kg and above) and rabbits (at 80 mg/kg and above). ^1

Animal reproduction studies conducted in pregnant rabbits (gestation days 6 to 19) administered intravenous NADA at 1680 mg/kg (32 times the maximum daily human dose or greater based on AUC levels of NADA) resulted in fetal scoliosis and a spectrum of cardiovascular malformations. Increased incidence of delayed or incomplete ossifications of the metacarpals/metatarsals/phalanges and increased ossification (fused jugal/maxilla bones) were also observed in rabbits at 1680 mg/kg without maternal toxicity. No adverse developmental outcomes were observed in rabbits administered intravenous NADA at 560 mg/kg (11 times the maximum daily human dose based on AUC levels of NADA). In reproduction studies in pregnant rats (gestation days 6 to 17) administered intravenous NADA at 3780 mg/kg (20 times the maximum daily human dose based on AUC levels of NADA) no fetal adverse effects were observed. Maternal toxicity, including increased incidence of litter loss, was observed in rats at 3780 mg/kg [see Clinical Pharmacology (12.3)].

No animal studies have been conducted to evaluate the potential reproductive and embryo-fetal effects of TYZAVAN (with the excipient NADA).

8.2 Lactation

Risk Summary

Vancomycin is present in human milk following intravenous administration, however, there are insufficient data to inform the levels. There are no data on the effects of vancomycin on the breastfed infant or milk production. The developmental and health benefits of breastfeeding should be considered along with the mother's clinical need for TYZAVAN and any potential adverse effects on the breastfed infant from TYZAVAN or from the underlying maternal condition.

8.4 Pediatric Use

TYZAVAN is indicated in pediatric patients (1 month and older) for the treatment of septicemia, infective endocarditis, skin and skin structure infections, bone infections and lower respiratory tract infections for whom appropriate dosing with this formulation can be achieved [see Indications and Usage (1.1 to 1.5) and Dosage and Administration (2.1, 2.3)].

Because of the limitations of the available strengths and administration requirements (i.e., administration of fractional doses is not recommended) of TYZAVAN, and to avoid unintentional overdose, this product is not recommended for use if a dose of TYZAVAN that does not equal 500 mg, 750 mg, 1 g, 1.25 g, 1.5 g, 1.75 g and 2 g is required, and an alternative formulation of vancomycin should be considered [see Dosage and Administration (2.1, 2.3)].

More severe infusion related reactions related to vancomycin administration may occur in pediatric patients. In pediatric patients, monitor vancomycin serum concentration and renal function when administering TYZAVAN [see Dosage and Administration (2.3) and Warnings and Precautions (5.1)]. Concomitant administration of vancomycin and intravenous anesthetic agents has been associated with erythema and histamine-like flushing in all patients including pediatric patients [see Warnings and Precautions (5.1)].

8.5 Geriatric Use

TYZAVAN is known to be substantially excreted by the kidney, and the risk of adverse reactions to this drug may be greater in patients with impaired renal function. Because elderly patients are more likely to have decreased renal function, care should be taken in dose selection [see Dosage and Administration (2.4)], and it may be useful to monitor renal function [see Warnings and Precautions (5.2)].

8.6 Renal Impairment

Dosage adjustment of Vancomycin Injection must be made in patients with impaired renal function [see Dosage and Administration (2.4)]. Measure trough vancomycin serum concentrations to guide intravenous therapy, especially in patients with impaired renal function or fluctuating renal function.

10 OVERDOSAGE

Supportive care is advised, with maintenance of glomerular filtration. Vancomycin is poorly removed by dialysis.

Hemofiltration and hemoperfusion with polysulfone resin have been reported to result in increased vancomycin clearance.

For current information on the management of overdosage, contact the National Poison Control Center at 1-800-222-1222 or www.poison.org.

11 DESCRIPTION

TYZAVAN (Vancomycin Injection, USP), in single-dose flexible bags contain vancomycin as vancomycin hydrochloride. It is a tricyclic glycopeptide antibacterial drug derived from Amycolatopsis orientalis (formerly Nocardia orientalis). The chemical name is (Sa)-(3S,6R,7R,22R,23S,26S,36R,38aR)-44-{[2-O-(3-amino-2,3,6-trideoxy-3-C-methyl-α-L-lyxo-hexopyranosyl)-β-D-glucopyranosyl]-oxy}-3-(carbamoylmethyl)-10,19-dichloro-2,3,4,5,6,7,23,24,25,26,36,37,38,38a-tetradecahydro-7,22,28,30,32-pentahydroxy-6-[(2R)-4-methyl-2-(methylamino]valeramido]-2,5,24,38,39-pentaoxo-22H-8,11:18,21-dietheno-23,36(iminometha-no)-13,16:31,35-dimetheno-1H,16H-[1,6,9]-oxadiazacyclohexadecino-[4,5-m][10,2,16]-benzoxa-diazacyclotetracosine-26-carboxylic acid, monohydrochloride. The molecular formula is C66H75Cl2N9O24•HCl and the molecular weight is 1,485.71. Vancomycin hydrochloride has the following structural formula:

TYZAVAN (Vancomycin Injection, USP), in single-dose flexible bags are sterile, nonpyrogenic premixed 100 mL, 150 mL, 200 mL, 250 mL, 300 mL, 350 mL or 400 mL solution containing 500 mg, 750 mg, 1 g, 1.25 g, 1.5 g, 1.75 g or 2 g vancomycin, respectively, as vancomycin hydrochloride. Each 100 mL of solution contains 1.36 g N-acetyl-D-alanine, 1.26 g L-lysine hydrochloride (monochloride) in water for injection. Hydrochloric acid and sodium hydroxide are used for pH adjustment. The pH is 4.5 to 5.5 and the osmolarity is 350 to 475 mOsmol/L.

12 CLINICAL PHARMACOLOGY

12.1 Mechanism of Action

Vancomycin is an antibacterial drug [see Microbiology (12.4)].

12.2 Pharmacodynamics

Based on animal models of infection, the antimicrobial activity of vancomycin appears to correlate with the AUC/MIC (area under the concentration-time curve/minimum inhibitory concentration) ratio for certain pathogens, including methicillin resistant Staphylococcus aureus. The principal pharmacokinetic/pharmacodynamic parameter best associated with clinical and microbiological cure has not been elucidated in clinical trials ^2,3.

12.3 Pharmacokinetics

General Pharmacokinetics

In subjects with normal kidney function, multiple intravenous dosing of 1 g of vancomycin (15 mg/kg) infused over 60 minutes produces mean plasma concentrations of approximately 63 mcg/mL immediately after the completion of infusion, mean plasma concentrations of approximately 23 mcg/mL 2 hours after infusion, and mean plasma concentrations of approximately 8 mcg/mL 11 hours after the end of the infusion.

Multiple dosing of 500 mg infused over 30 minutes produces mean plasma concentrations of about 49 mcg/mL at the completion of infusion, mean plasma concentrations of about 19 mcg/mL 2 hours after infusion, and mean plasma concentrations of about 10 mcg/mL 6 hours after infusion. The plasma concentrations during multiple dosing are similar those after a single dose.

In healthy subjects administered a single 1g dose of TYZAVAN, geometric mean (geometric %CV) AUC0-inf values for NADA and vancomycin were 209 (19.6%) and 219 (13.7%) mcg*h/mL, respectively. Based on a population pharmacokinetic analysis, 1g TYZAVAN administered over 1.5 hours every 12 hours achieves a geometric mean (95% prediction interval) steady state AUC0-24 exposure of 383 (277-547) and 382 (261-567) mcg*h/mL for NADA and vancomycin in healthy subjects, respectively.

Distribution

The distribution coefficient is from 0.3 to 0.43 L/kg. Vancomycin is approximately 55% serum protein bound as measured by ultrafiltration at vancomycin serum concentrations of 10 to 100 mcg/mL. After intravenous administration of vancomycin, inhibitory concentrations are present in pleural, pericardial, ascitic, and synovial fluids; in urine; in peritoneal dialysis fluid; and in atrial appendage tissue. Vancomycin does not readily diffuse across normal meninges into the spinal fluid; but, when the meninges are inflamed, penetration into the spinal fluid occurs.

Elimination

Mean plasma clearance is about 0.058 L/kg/h, and mean renal clearance is about 0.048 L/kg/h. The mean elimination half-life of vancomycin from plasma is 4 to 6 hours in subjects with normal renal function. In anephric patients, the mean elimination half-life is 7.5 days. Total systemic and renal clearance of vancomycin may be reduced in the elderly.

Metabolism

There is no apparent metabolism of the vancomycin.

Excretion

In the first 24 hours, about 75% of an administered dose of vancomycin is excreted in urine by glomerular filtration. Renal dysfunction slows excretion of vancomycin.

In the first 48 hours after intravenous administration of a single 1 g dose of TYZAVAN, the percent excreted unchanged in urine was approximately 80% for NADA.

12.4 Microbiology

Mechanism of Action

The bactericidal action of vancomycin results primarily from inhibition of cell-wall biosynthesis. In addition, vancomycin alters bacterial-cell-membrane permeability and RNA synthesis.

Resistance

There is no cross-resistance between vancomycin and other antibacterial(s). Vancomycin is not active in vitro against gram-negative bacilli, mycobacteria, or fungi.

Interaction with Other Antimicrobials

The combination of vancomycin and an aminoglycoside acts synergistically in vitro against many isolates of Staphylococcus aureus, Streptococcus gallolyticus (previously known as Streptococcus bovis), Enterococcus spp, and the viridans group streptococci.

Antimicrobial Activity

Vancomycin has been shown to be active against most isolates of the following bacteria, both in vitro and in clinical infections [see Indications and Usage (1)].

Aerobic bacteria

Gram-positive bacteria

Corynebacterium spp.

Enterococcus spp. (including Enterococcus faecalis)

Staphylococcus aureus (including methicillin-resistant and methicillin-susceptible isolates)

Coagulase negative staphylococci (including S. epidermidis and methicillin-resistant isolates)

Streptococcus gallolyticus (previously known as Streptococcus bovis)

Viridans group streptococci

The following in vitro data are available, but their clinical significance is unknown.

At least 90 percent of the following bacteria exhibit an in vitro minimum inhibitory concentration (MIC) less than or equal to the susceptible breakpoint for vancomycin against isolates of similar genus or organism group. However, the efficacy of vancomycin in treating clinical infections caused by these bacteria has not been established in adequate and well-controlled clinical trials.

Aerobic bacteria

Gram-positive bacteria

Listeria monocytogenes

Streptococcus pyogenes

Streptococcus pneumoniae

Streptococcus agalactiae

Anaerobic bacteria

Gram-positive bacteria

Actinomyces spp.

Lactobacillus spp.

Susceptibility Testing

For specific information regarding susceptibility test interpretive criteria and associated test methods and quality control standards recognized by FDA for this drug, please see: https://www.fda.gov/STIC.

13 NONCLINICAL TOXICOLOGY

13.1 Carcinogenesis, Mutagenesis, Impairment of Fertility

No long-term studies in animals have been performed to evaluate carcinogenic potential. No definitive fertility studies have been performed.

13.2 Animal Toxicology and/or Pharmacology

In animal studies, hypotension and bradycardia occurred in dogs receiving an intravenous infusion of vancomycin 25 mg/kg, at a concentration of 25 mg/mL and an infusion rate of 13.3 mL/min.

15 REFERENCES

1. Byrd RA., Gries CL, Buening M.: Developmental Toxicology Studies of Vancomycin Hydrochloride Administered Intravenously to Rats and Rabbits. Fundam Appl Toxicol 1994; 23: 590-597.

2. Rybak MJ. The pharmacokinetic and pharmacodynamic properties of vancomycin. Clinical Infectious Diseases. 2006;42(Supplement_1): S35-S39.

3. Rybak MJ, Le J, Lodise TP, et al. Therapeutic monitoring of vancomycin for serious methicillin-resistant Staphylococcus aureus infections: a revised consensus guideline and review by the American Society of Health-System Pharmacists, the Infectious Diseases Society of America, the Pediatric Infectious Diseases Society, and the Society of Infectious Diseases Pharmacists. Clinical Infectious Diseases. 2020;71(6):1361-1364.

16 HOW SUPPLIED/STORAGE AND HANDLING

16.1 How Supplied

TYZAVAN (Vancomycin Injection, USP) is supplied as a ready to use clear, colorless to light brown solution in single-dose flexible bags containing 500 mg, 750 mg, 1 g, 1.25 g, 1.5 g, 1.75 g and 2 g vancomycin in 100 mL, 150 mL, 200 mL, 250 mL, 300 mL, 350 mL and 400 mL of liquid (consists of water for injection together with the excipients NADA and lysine) [see Description (11)]. The flexible bags are supplied in sealed aluminum overpouches. The bags are supplied in the following packages described in table 1 below:

Table 1: TYZAVAN PACKAGE INFORMATION
Strength of TYZAVAN | NDC number | Packaging configuration
500 mg/100 mL (5 mg/mL) | 0143-9471-06 | Carton of 6 bags
500 mg/100 mL (5 mg/mL) | 0143-9471-12 | Carton of 12 bags
750 mg/150 mL (5 mg/mL) | 0143-9468-06 | Carton of 6 bags
750 mg/150 mL (5 mg/mL) | 0143-9468-12 | Carton of 12 bags
1 g/200 mL (5 mg/mL) | 0143-9472-06 | Carton of 6 bags
1 g/200 mL (5 mg/mL) | 0143-9472-12 | Carton of 12 bags
1.25 g/250 mL (5 mg/mL) | 0143-9466-06 | Carton of 6 bags
1.5 g/300 mL (5 mg/mL) | 0143-9469-06 | Carton of 6 bags
1.75 g/350 mL (5 mg/mL) | 0143-9467-06 | Carton of 6 bags
2 g/400 mL (5 mg/mL) | 0143-9470-06 | Carton of 6 bags

16.2 Storage

Store at 15°C to 25°C (59°F to 77ºF), in original package. Use within 28 days of removal from aluminum overpouch.

17 PATIENT COUNSELING INFORMATION

Infusion Reactions During or After Intravenous Use

Advise patients that generalized skin redness, skin rash, itching, flushing, muscle pain, chest pain, shortness of breath, wheezing, or dizziness may occur during intravenous infusion of TYZAVAN. These reactions can be lessened or prevented by infusing the drug over at least 60 minutes [see Warnings and Precautions (5.1)].

Acute Kidney Injury

Advise patients that TYZAVAN can result in kidney damage and that blood tests are required to monitor vancomycin blood levels and kidney function during therapy [see Warnings and Precautions (5.2)].

Hearing Loss or Balance Problems

Advise patients that TYZAVAN may result in decreased hearing and to report hearing loss or balance problems to their healthcare provider [see Warnings and Precautions (5.3)].

Severe Dermatologic Reactions

Advise patients about the signs and symptoms of serious skin manifestations. Instruct patients to stop TYZAVAN immediately and promptly seek medical attention at the first signs or symptoms of skin rash, mucosal lesions and blisters to their healthcare provider [see Warnings and Precautions (5.4)].

Diarrhea

Diarrhea is a common problem caused by antibacterial drugs, including TYZAVAN, which usually ends when the antibacterial drug is discontinued. Sometimes after starting treatment with antibacterial drugs, patients can develop watery and bloody stools (with or without stomach cramps and fever) even as late as two or more months after having taken the last dose of the antibacterial drug. If this occurs, patients should contact their physician as soon as possible [see Warnings and Precautions (5.5)].

Antibacterial Resistance

Patients should be counseled that antibacterial drugs including TYZAVAN, should only be used to treat bacterial infections. They do not treat viral infections (e.g., the common cold). When TYZAVAN is prescribed to treat a bacterial infection, patients should be told that although it is common to feel better early in the course of therapy, the medication should be taken exactly as directed. Skipping doses or not completing the full course of therapy may (1) decrease the effectiveness of the immediate treatment and (2) increase the likelihood that bacteria will develop resistance and will not be treatable by TYZAVAN or other antibacterial drugs in the future.

Manufactured for:

Hikma Pharmaceuticals USA, Inc.

Berkeley Heights, NJ 07922

Made in Switzerland

L130USTZV01

PRINCIPAL DISPLAY PANEL - 500 mg/100 mL

NDC 0143-9471-01
LOT
EXP
Rx Only

NEW
FORMULATION

TYZAVAN
(vancomycin injection, USP)
500 mg/100 mL (5 mg/mL)

Single-Dose Flexible Bag
Sterile, Nonpyrogenic

Dosage: See Prescribing Information.
For Intravenous Use Only
Infuse over at least 60 minutes.
Cautions: Do not add supplementary medication or
additives. Discard unused portion.
Store at 15°C to 25°C (59°F to 77°F), in original package.
Use within 28 days of removal from aluminum overpouch.
100 mL contains: Vancomycin hydrochloride equivalent
to 500 mg vancomycin; 1.36 g N-acetyl-D-alanine and
1.26 g L-lysine hydrochloride in water for injection.
pH may have been adjusted with hydrochloric acid
and/or sodium hydroxide.

Manufactured for Hikma Pharmaceuticals USA, Inc.
Berkeley Heights, NJ 07922

500 mg

Ready
To Use

NEW
FORMULATION

Made in Switzerland
BH130USTZV100

Rev. March 2025

Outlet port

NDC 0143-9471-01
Rx Only

TYZAVAN
(vancomycin injection, USP)
500 mg/100 mL (5 mg/mL)

Single-Dose Flexible Bag
Sterile, Nonpyrogenic

NEW FORMULATION
Ready To Use

Dosage: See Prescribing Information.
For Intravenous Infusion Only
Infuse over at least 60 minutes.

500 mg

Cautions:
Do not add supplementary medication
or additives. Discard unused portion.

Store at 15°C to 25°C (59°F to 77°F), in original package.
Use within 28 days of removal from aluminum overpouch.

100 mL contains: Vancomycin hydrochloride equivalent
to 500 mg vancomycin; 1.36 g N-acetyl-D-alanine and
1.26 g L-lysine hydrochloride in water for injection.
pH may have been adjusted with hydrochloric acid
and/or sodium hydroxide.

Manufactured for Hikma Pharmaceuticals USA, Inc.
Berkeley Heights, NJ 07922

Made in Switzerland
Rev. March 2025

Hikma

0130USTZV100

Rx Only
Sterile

NDC 0143-9471-06
Contains six (6) single-dose
Flexible Bags of NDC 0143-9471-01

Ready
To Use

TYZAVAN
(vancomycin injection, USP)
500 mg/100 mL (5 mg/mL)

For Intravenous Use Only
Store at 15°F to 25°C (59°F to 77°F), in original package.
Discard unused portion.

500 mg

NEW FORMULATION

Rx Only
Sterile

NDC 0143-9471-12
Contains six (12) single-dose
Flexible Bags of NDC 0143-9471-01

Ready
To Use

TYZAVAN
(vancomycin injection, USP)
500 mg/100 mL (5 mg/mL)

For Intravenous Infusion Only
Store at 15°F to 25°C (59°F to 77°F), in original package.
Discard unused portion.

500 mg

NEW FORMULATION

PRINCIPAL DISPLAY PANEL - 750 mg/150 mL

NDC 0143-9468-01
EXP
Rx Only

NEW
FORMULATION

TYZAVAN
(vancomycin injection, USP)
750 mg/150 mL (5 mg/mL)

Single-Dose Flexible Bag
Sterile, Nonpyrogenic

Dosage: See Prescribing Information.
For Intravenous Infusion Only
Infuse over at least 60 minutes.
Cautions: Do not add supplementary medication or
additives. Discard unused portion.
Store at 15°C to 25°C (59°F to 77°F), in original package.
Use within 28 days of removal from aluminum overpouch.
100 mL contains: Vancomycin hydrochloride equivalent
to 500 mg vancomycin; 1.36 g N-acetyl-D-alanine and
1.26 g L-lysine hydrochloride in water for injection.
pH may have been adjusted with hydrochloric acid
and/or sodium hydroxide.

Manufactured for Hikma Pharmaceuticals USA, Inc.
Berkeley Heights, NJ 07922

750 mg

Ready
To Use

NEW
FORMULATION

Made in Switzerland
BH130USTZV150

Rev. March 2025

Outlet port

NDC 0143-9468-01
Rx Only

TYZAVAN
(vancomycin injection, USP)
750 mg/150 mL (5 mg/mL)

Single-Dose Flexible Bag
Sterile, Nonpyrogenic

NEW FORMULATION
Ready To Use

Dosage: See Prescribing Information.
For Intravenous Infusion Only
Infuse over at least 60 minutes.

750 mg

Cautions:
Do not add supplementary medication
or additives. Discard unused portion.

Store at 15°C to 25°C (59°F to 77°F), in original package.
Use within 28 days of removal from aluminum overpouch.

100 mL contains: Vancomycin hydrochloride equivalent
to 500 mg vancomycin; 1.36 g N-acetyl-D-alanine and
1.26 g L-lysine hydrochloride in water for injection.
pH may have been adjusted with hydrochloric acid
and/or sodium hydroxide.

Manufactured for Hikma Pharmaceuticals USA, Inc.
Berkeley Heights, NJ 07922

Made in Switzerland
Rev. March 2025

Hikma

0130USTZV150

Rx Only
Sterile

NDC 0143-9468-06
Contains six (6) single-dose
Flexible Bags of NDC 0143-9468-01

Ready
To Use

TYZAVAN
(vancomycin injection, USP)
750 mg/150 mL (5 mg/mL)

For Intravenous Infusion Only
Store at 15°F to 25°C (59°F to 77°F), in original package.
Discard unused portion.

750
mg

NEW FORMULATION

Rx Only
Sterile

NDC 0143-9468-12
Contains twelve (12) single-dose
Flexible Bags of NDC 0143-9468-01

Ready
To Use

TYZAVAN
(vancomycin injection, USP)
750 mg/150 mL (5 mg/mL)

For Intravenous Infusion Only
Store at 15°F to 25°C (59°F to 77°F), in original package.
Discard unused portion.

750
mg

NEW FORMULATION

PRINCIPAL DISPLAY PANEL - 1g/200mL

NDC 0143-9472-01
LOT
EXP
Rx Only

NEW
FORMULATION

TYZAVAN

(vancomycin injection, USP)
1 g/200 mL (5 mg/mL)

Single-Dose Flexible Bag
Sterile, Nonpyrogenic

Dosage: See Prescribing Information.
For Intravenous Infusion Only
Infuse over at least 60 minutes.
Cautions: Do not add supplementary medication or
additives. Discard unused portion.
Store at 15°C to 25°C (59°F to 77°F), in original package.
Use within 28 days of removal from aluminum overpouch.
Each 100 mL contains: Vancomycin hydrochloride equivalent
to 500 mg vancomycin; 1.36 g N-acetyl-D-alanine and
1.26 g L-lysine hydrochloride in water for injection.
pH may have been adjusted with hydrochloric acid
and/or sodium hydroxide.

Manufactured for Hikma Pharmaceuticals USA, Inc.
Berkeley Heights, NJ 07922

1 g

Ready
To Use

NEW
FORMULATION

Made in Switzerland
BH130USTZV200

Rev. March 2025

Outlet port

NDC 0143-9472-01
Rx Only

TYZAVAN
(vancomycin injection, USP)
1 g/200 mL (5 mg/mL)

Single-Dose Flexible Bag
Sterile, Nonpyrogenic

NEW FORMULATION
Ready To Use

Dosage: See Prescribing Information.
For Intravenous Infusion Only
Infuse over at least 60 minutes.

1 g

Cautions:
Do not add supplementary medication
or additives. Discard unused portion.

Store at 15°C to 25°C (59°F to 77°F), in original package.
Use within 28 days of removal from aluminum overpouch.

Each 100 mL contains: Vancomycin hydrochloride equivalent
to 500 mg vancomycin; 1.36 g N-acetyl-D-alanine and
1.26 g L-lysine hydrochloride in water for injection.
pH may have been adjusted with hydrochloric acid
and/or sodium hydroxide.

Manufactured for Hikma Pharmaceuticals USA, Inc.
Berkeley Heights, NJ 07922

Made in Switzerland
Rev. March 2025

Hikma

O130USTZV200

Rx Only
Sterile

NDC 0143-9472-06
Contains six (6) single-dose
Flexible Bags of NDC 0143-9472-01

Ready
To Use

TYZAVAN
(vancomycin injection, USP)
1 g/200 mL (5 mg/mL)

For Intravenous Infusion Only
Store at 15°F to 25°C (59°F to 77°F), in original package.
Discard unused portion.

1 g

NEW FORMULATION

Rx Only
Sterile

NDC 0143-9472-12
Contains twelve (12) single-dose
Flexible Bags of NDC 0143-9472-01

Ready
To Use

TYZAVAN
(vancomycin injection, USP)
1 g/200 mL (5 mg/mL)

For Intravenous Infusion Only
Store at 15°F to 25°C (59°F to 77°F), in original package.
Discard unused portion.

1 g

NEW FORMULATION

PRINCIPAL DISPLAY PANEL - 1.25g/250mL

NDC 0143-9466-01
LOT
EXP
Rx Only

NEW
FORMULATION

TYZAVAN
(vancomycin injection, USP)
1.25 g/250 mL (5 mg/mL)

Single-Dose Flexible Bag
Sterile, Nonpyrogenic

Dosage: See Prescribing Information.
For Intravenous Infusion Only
Infuse over at least 60 minutes.
Cautions: Do not add supplementary medication or
additives. Discard unused portion.
Store at 15°C to 25°C (59°F to 77°F), in original package.
Use within 28 days of removal from aluminum overpouch.
Each 100 mL contains: Vancomycin hydrochloride equivalent
to 500 mg vancomycin; 1.36 g N-acetyl-D-alanine and
1.26 g L-lysine hydrochloride in water for injection.
pH may have been adjusted with hydrochloric acid
and/or sodium hydroxide.

Manufactured for Hikma Pharmaceuticals USA, Inc.
Berkeley Heights, NJ 07922

1.25 g

Ready
To Use

NEW
FORMULATION

Made in Switzerland
BH130USTZV250

Rev. March 2025

Outlet port

NDC 0143-9466-01
Rx Only

TYZAVAN
(vancomycin injection, USP)
1.25 g/250 mL (5 mg/mL)

Single-Dose Flexible Bag
Sterile, Nonpyrogenic

NEW FORMULATION
Ready To Use

Dosage: See Prescribing Information.
For Intravenous Infusion Only
Infuse over at least 60 minutes.

1.25 g

Cautions:
Do not add supplementary medication
or additives. Discard unused portion.

Store at 15°C to 25°C (59°F to 77°F), in original package.
Use within 28 days of removal from aluminum overpouch.

Each 100 mL contains: Vancomycin hydrochloride equivalent
to 500 mg vancomycin; 1.36 g N-acetyl-D-alanine and
1.26 g L-lysine hydrochloride in water for injection.
pH may have been adjusted with hydrochloric acid
and/or sodium hydroxide.

Manufactured for Hikma Pharmaceuticals USA, Inc.
Berkeley Heights, NJ 07922

Made in Switzerland
Rev. March 2025

Hikma

0130USTZV250

Rx Only
Sterile

NDC 0143-9466-06
Contains six (6) single-dose
Flexible Bags of NDC 0143-9466-01

Ready
To Use

TYZAVAN
(vancomycin injection, USP)
1.25 g/250 mL (5 mg/mL)

For Intravenous Infusion Only
Store at 15°F to 25°C (59°F to 77°F), in original package.
Discard unused portion.

1.25 g

NEW FORMULATION

PRINCIPAL DISPLAY PANEL - 1.5g/300mL

NDC 0143-9469-01
LOT
EXP
Rx Only

NEW
FORMULATION

TYZAVAN
(vancomycin injection, USP)
1.5 g/300 mL (5 mg/mL)

Single-Dose Flexible Bag
Sterile, Nonpyrogenic

Dosage: See Prescribing Information.
For Intravenous Infusion Only
Infuse over at least 60 minutes.
Cautions: Do not add supplementary medication or
additives. Discard unused portion.
Store at 15°C to 25°C (59°F to 77°F), in original package.
Use within 28 days of removal from aluminum overpouch.
Each 100 mL contains: Vancomycin hydrochloride equivalent
to 500 mg vancomycin; 1.36 g N-acetyl-D-alanine and
1.26 g L-lysine hydrochloride in water for injection.
pH may have been adjusted with hydrochloric acid
and/or sodium hydroxide.

Manufactured for Hikma Pharmaceuticals USA, Inc.
Berkeley Heights, NJ 07922

1.5 g

Ready
To Use

NEW
FORMULATION

Made in Switzerland
BH130USTZV300

Rev. March 2025

Outlet port

NDC 0143-9469-01
Rx Only

TYZAVAN
(vancomycin injection, USP)
1.5 g/300 mL (5 mg/mL)

Single-Dose Flexible Bag
Sterile, Nonpyrogenic

NEW FORMULATION
Ready To Use

Dosage: See Prescribing Information.
For Intravenous Infusion Only
Infuse over at least 60 minutes.

1.5 g

Cautions:
Do not add supplementary medication
or additives. Discard unused portion.

Store at 15°C to 25°C (59°F to 77°F), in original package.
Use within 28 days of removal from aluminum overpouch.

Each 100 mL contains: Vancomycin hydrochloride equivalent
to 500 mg vancomycin; 1.36 g N-acetyl-D-alanine and
1.26 g L-lysine hydrochloride in water for injection.
pH may have been adjusted with hydrochloric acid
and/or sodium hydroxide.

Manufactured for Hikma Pharmaceuticals USA, Inc.
Berkeley Heights, NJ 07922

Made in Switzerland
Rev. March 2025

Hikma

0130USTZV300

Rx Only
Sterile

NDC 0143-9469-06
Contains six (6) single-dose
Flexible Bags of NDC 0143-9469-01

Ready
To Use

TYZAVAN
(vancomycin injection, USP)
1.5 g/300 mL (5 mg/mL)

For Intravenous Infusion Only
Store at 15°F to 25°C (59°F to 77°F), in original package.
Discard unused portion.

1.5 g

NEW FORMULATION

PRINCIPAL DISPLAY PANEL - 1.75g/350mL

NDC 0143-9467-01
LOT
EXP
Rx Only

NEW
FORMULATION

TYZAVAN
(vancomycin injection, USP)
1.75 g/350 mL (5 mg/mL)

Single-Dose Flexible Bag
Sterile, Nonpyrogenic

Dosage: See Prescribing Information.
For Intravenous Infusion Only
Infuse over at least 60 minutes.
Cautions: Do not add supplementary medication or
additives. Discard unused portion.
Store at 15°C to 25°C (59°F to 77°F), in original package.
Use within 28 days of removal from aluminum overpouch.
Each 100 mL contains: Vancomycin hydrochloride equivalent
to 500 mg vancomycin; 1.36 g N-acetyl-D-alanine and
1.26 g L-lysine hydrochloride in water for injection.
pH may have been adjusted with hydrochloric acid
and/or sodium hydroxide.

Manufactured for Hikma Pharmaceuticals USA, Inc.
Berkeley Heights, NJ 07922

1.75 g

Ready
To Use

NEW
FORMULATION

Made in Switzerland
BH130USTZV350

Rev. March 2025

Outlet port

NDC 0143-9467-01
Rx Only

TYZAVAN
(vancomycin injection, USP)
1.75 g/350 mL (5 mg/mL)

Single-Dose Flexible Bag
Sterile, Nonpyrogenic

NEW FORMULATION
Ready To Use

Dosage: See Prescribing Information.
For Intravenous Infusion Only
Infuse over at least 60 minutes.

1.75 g

Cautions:
Do not add supplementary medication
or additives. Discard unused portion.

Store at 15°C to 25°C (59°F to 77°F), in original package.
Use within 28 days of removal from aluminum overpouch.

Each 100 mL contains: Vancomycin hydrochloride equivalent
to 500 mg vancomycin; 1.36 g N-acetyl-D-alanine and
1.26 g L-lysine hydrochloride in water for injection.
pH may have been adjusted with hydrochloric acid
and/or sodium hydroxide.

Manufactured for Hikma Pharmaceuticals USA, Inc.
Berkeley Heights, NJ 07922

Made in Switzerland
Rev. March 2025

Hikma

0130USTZV350

Rx Only
Sterile

NDC 0143-9467-06
Contains six (6) single-dose
Flexible Bags of NDC 0143-9467-01

Ready
To Use

TYZAVAN
(vancomycin injection, USP)
1.75 g/350 mL (5 mg/mL)

For Intravenous Infusion Only
Store at 15°F to 25°C (59°F to 77°F), in original package.
Discard unused portion.

1.75 g

NEW FORMULATION

PRINCIPAL DISPLAY PANEL - 2 g/400mL

NDC 0143-9470-01
LOT
EXP
Rx Only

NEW
FORMULATION

TYZAVAN
(vancomycin injection, USP)
2 g/400 mL (5 mg/mL)

Single-Dose Flexible Bag
Sterile, Nonpyrogenic

Dosage: See Prescribing Information.
For Intravenous Infusion Only
Infuse over at least 60 minutes.
Cautions: Do not add supplementary medication or
additives. Discard unused portion.
Store at 15°C to 25°C (59°F to 77°F), in original package.
Use within 28 days of removal from aluminum overpouch.
Each 100 mL contains: Vancomycin hydrochloride equivalent
to 500 mg vancomycin; 1.36 g N-acetyl-D-alanine and
1.26 g L-lysine hydrochloride in water for injection.
pH may have been adjusted with hydrochloric acid
and/or sodium hydroxide.

Manufactured for Hikma Pharmaceuticals USA, Inc.
Berkeley Heights, NJ 07922

2 g

Ready
To Use

NEW
FORMULATION

Made in Switzerland
BH130USTZV400

Rev. March 2025

Outlet port

NDC 0143-9470-01
Rx Only

TYZAVAN
(vancomycin injection, USP)
2 g/400 mL (5 mg/mL)

Single-Dose Flexible Bag
Sterile, Nonpyrogenic

NEW FORMULATION
Ready To Use

Dosage: See Prescribing Information.
For Intravenous Infusion Only
Infuse over at least 60 minutes.

2 g

Cautions:
Do not add supplementary medication
or additives. Discard unused portion.

Store at 15°C to 25°C (59°F to 77°F), in original package.
Use within 28 days of removal from aluminum overpouch.

Each 100 mL contains: Vancomycin hydrochloride equivalent
to 500 mg vancomycin; 1.36 g N-acetyl-D-alanine and
1.26 g L-lysine hydrochloride in water for injection.
pH may have been adjusted with hydrochloric acid
and/or sodium hydroxide.

Manufactured for Hikma Pharmaceuticals USA, Inc.
Berkeley Heights, NJ 07922

Made in Switzerland
Rev. March 2025

Hikma

0130USTZV400

Rx Only
Sterile

NDC 0143-9470-06
Contains six (6) single-dose
Flexible Bags of NDC 0143-9470-01

Ready
To Use

TYZAVAN
(vancomycin injection, USP)
2 g/400 mL (5 mg/mL)

For Intravenous Infusion Only
Store at 15°F to 25°C (59°F to 77°F), in original package.
Discard unused portion.

2 g

NEW FORMULATION